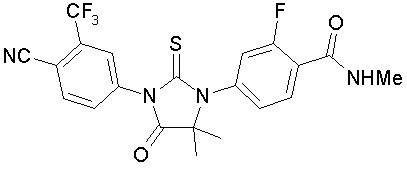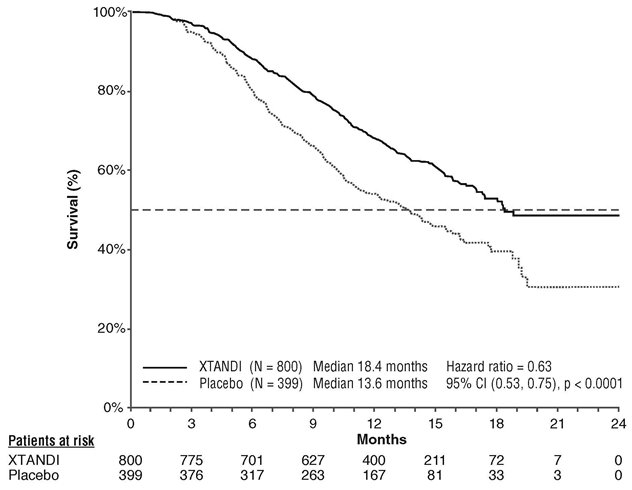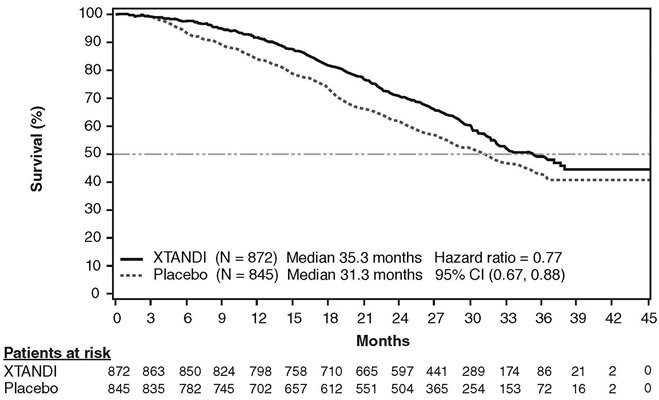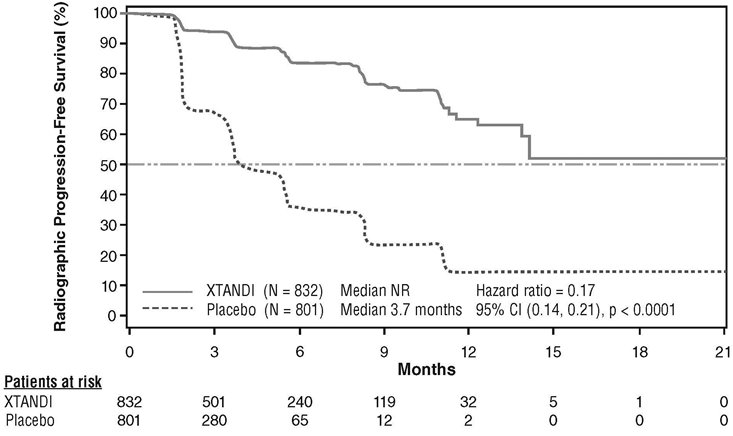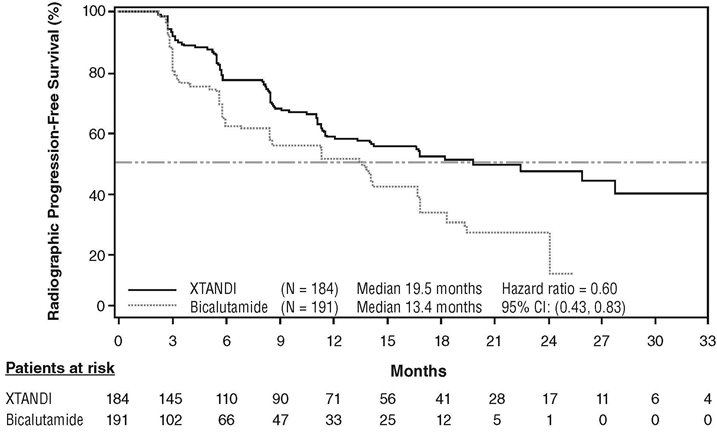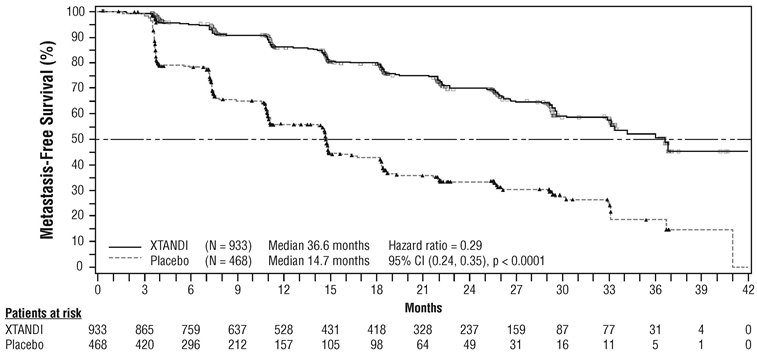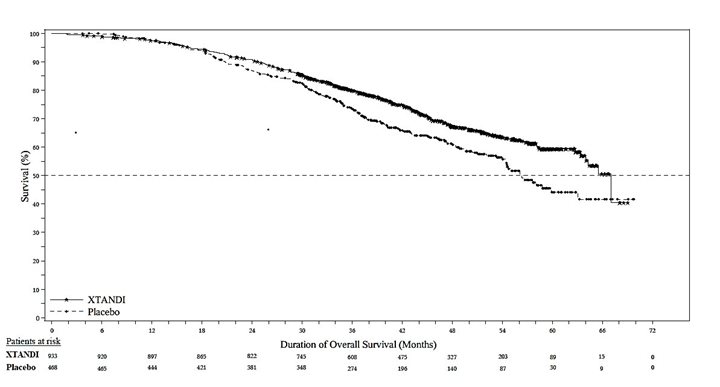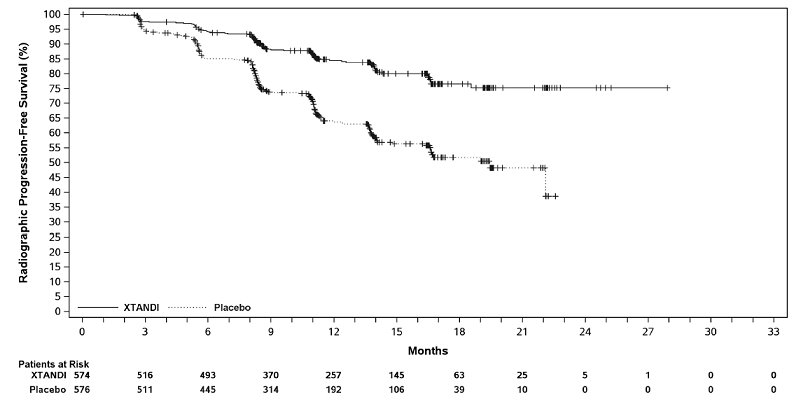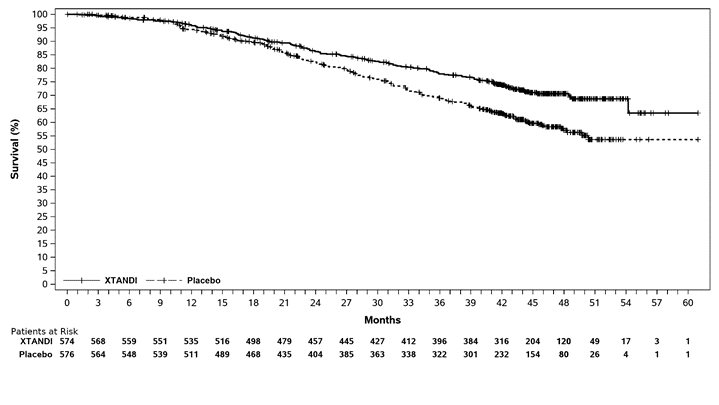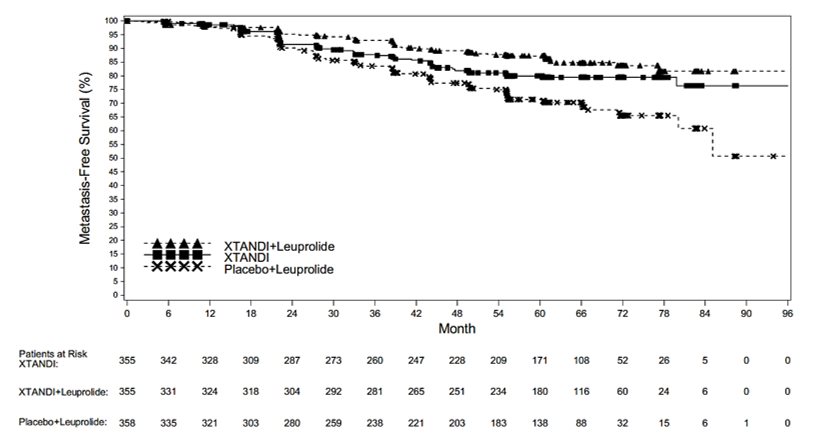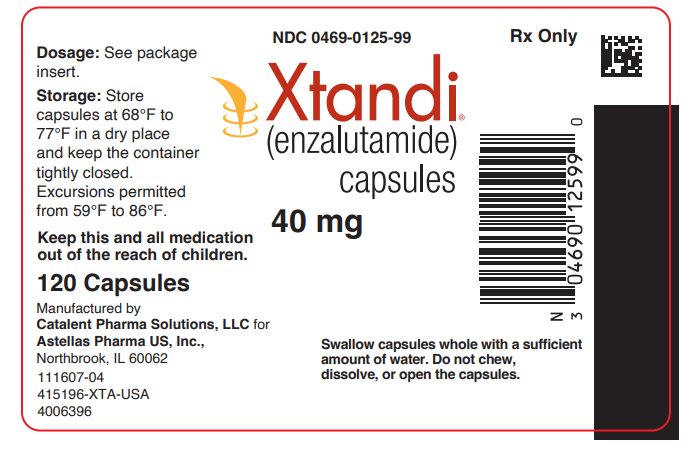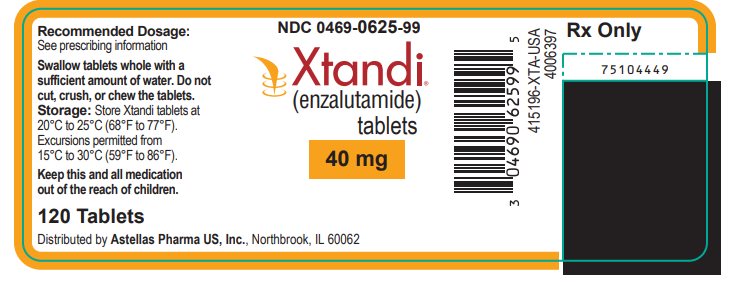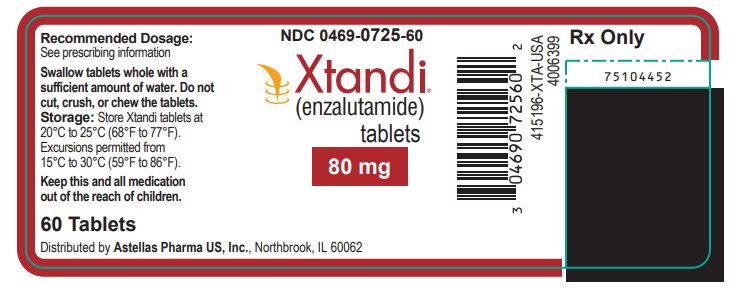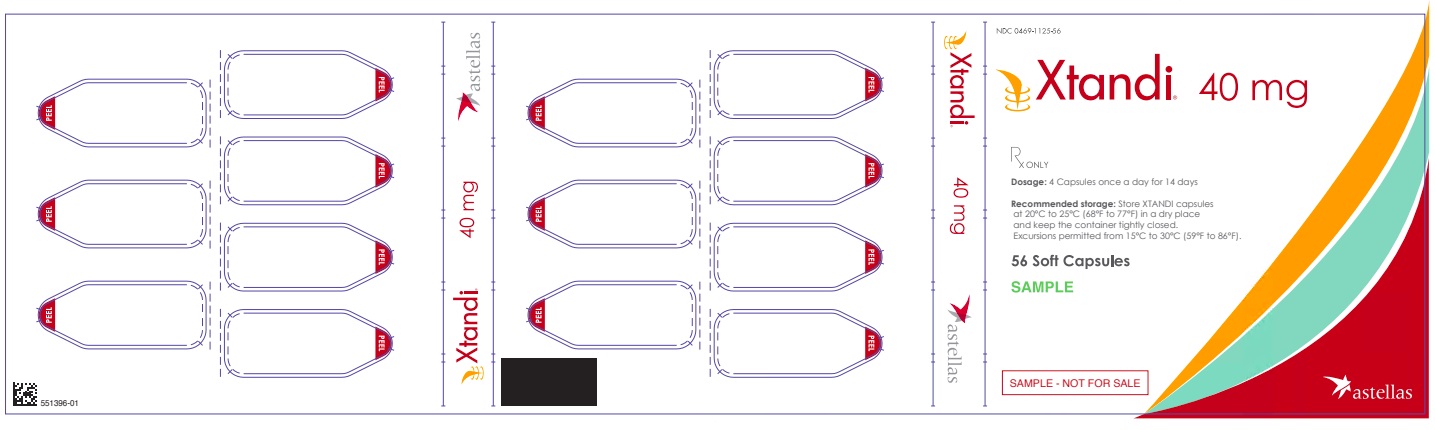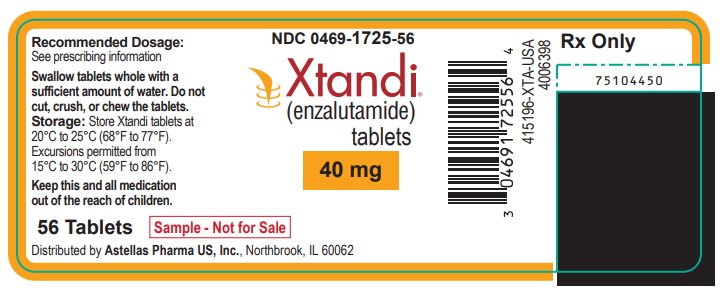 DRUG LABEL: Xtandi
NDC: 0469-0125 | Form: CAPSULE
Manufacturer: Astellas Pharma US, Inc.
Category: prescription | Type: HUMAN PRESCRIPTION DRUG LABEL
Date: 20251212

ACTIVE INGREDIENTS: ENZALUTAMIDE 40 mg/1 1

HIGHLIGHTS OF PRESCRIBING INFORMATION

These highlights do not include all the information needed to use XTANDI safely and effectively. See full prescribing information for XTANDI.
XTANDI® (enzalutamide) capsules, for oral use
XTANDI® (enzalutamide) tablets, for oral use
Initial U.S. Approval: 2012

RECENT MAJOR CHANGES

Dosage and Administration (2.1) | 1/2025
Warnings and Precautions (5.7); Warnings and Precautions (5.8) | 1/2025; 12/2025

1 INDICATIONS AND USAGE

XTANDI is an androgen receptor inhibitor indicated for the treatment of patients with:

- castration-resistant prostate cancer. (1)
- metastatic castration-sensitive prostate cancer. (1)
- non‑metastatic castration‑sensitive prostate cancer with biochemical recurrence at high risk for metastasis. (1)

2 DOSAGE AND ADMINISTRATION

- Take XTANDI 160 mg administered orally once daily with or without food. (2.1)
- Advise patients to take each capsule or tablet whole with a sufficient amount of water to ensure that all medication is successfully swallowed. (2.1, 5.7)
- Patients receiving XTANDI for castration-resistant prostate cancer, or metastatic castration sensitive prostate cancer should also receive a gonadotropin-releasing hormone (GnRH) analog concurrently or should have had bilateral orchiectomy. (2.1)
- Patients with non-metastatic castration-sensitive prostate cancer with biochemical recurrence at high risk for metastasis may be treated with or without a GnRH analog. (2.1)

3 DOSAGE FORMS AND STRENGTHS

- Capsules: 40 mg (3)
- Tablets: 40 mg, 80 mg (3)

4 CONTRAINDICATIONS

None. (4)

5 WARNINGS AND PRECAUTIONS

- Seizure occurred in 0.6% of patients receiving XTANDI. In patients with predisposing factors, seizures were reported in 2.2% of patients. Permanently discontinue XTANDI in patients who develop a seizure during treatment. (5.1)
- Posterior reversible encephalopathy syndrome (PRES): Discontinue XTANDI. (5.2)
- Hypersensitivity: Discontinue XTANDI. (5.3)
- Ischemic Heart Disease: Optimize management of cardiovascular risk factors. Discontinue XTANDI for Grade 3-4 adverse reactions (5.4)
- Falls and Fractures: Evaluate patients for fracture and fall risk, and treat patients with bone-targeted agents according to established guidelines. (5.5)
- Embryo-Fetal Toxicity: XTANDI can cause fetal harm and loss of pregnancy. Advise males with female partners of reproductive potential to use effective contraception. (5.6, 8.1, 8.3)
- Severe Dysphagia or Choking Related to Product Size: Consider using smaller XTANDI tablet(s) in patients who have difficulty swallowing. Discontinue XTANDI for patients who cannot swallow capsules or tablets. (2.1, 5.7)
- Interference with Immunoassay Measurement of Digoxin XTANDI can interfere with certain digoxin immunoassays, resulting in falsely elevated digoxin plasma concentration results. (5.8, 7.3)

6 ADVERSE REACTIONS

The most common adverse reactions (≥ 10%) that occurred more frequently (≥ 2% over placebo) in the XTANDI-treated patients are musculoskeletal pain, fatigue, hot flush, constipation, decreased appetite, diarrhea, hypertension, hemorrhage, fall, fracture, and headache. (6.1)

To report SUSPECTED ADVERSE REACTIONS, contact Astellas Pharma US, Inc. at 1-800-727-7003 or FDA at 1-800-FDA-1088 or www.fda.gov/medwatch.

7 DRUG INTERACTIONS

- Strong CYP2C8 Inhibitors: Avoid strong CYP2C8 inhibitors. If coadministration cannot be avoided, reduce the dosage of XTANDI. (2.3, 7.1)
- Strong CYP3A4 Inducers: Avoid strong CYP3A4 inducers. If coadministration cannot be avoided, increase the dosage of XTANDI. (2.3, 7.1)
- Avoid coadministration with certain CYP3A4, CYP2C9, or CYP2C19 substrates for which a minimal decrease in concentration may lead to therapeutic failure of the substrate. In cases where active metabolites are formed, there may be increased exposure to the active metabolites. (7.2)

FULL PRESCRIBING INFORMATION

1 INDICATIONS AND USAGE

XTANDI® is indicated for the treatment of patients with:

- castration-resistant prostate cancer (CRPC)
- metastatic castration-sensitive prostate cancer (mCSPC)
- non‑metastatic castration‑sensitive prostate cancer (nmCSPC) with biochemical recurrence at high risk for metastasis (high-risk BCR)

2 DOSAGE AND ADMINISTRATION

2.1 Recommended Dosage

The recommended dosage of XTANDI is 160 mg administered orally once daily with or without food [see Clinical Pharmacology (12.3)] until disease progression or unacceptable toxicity.

Advise patients to take each capsule or tablet whole with a sufficient amount of water to ensure that all medication is successfully swallowed. Do NOT chew, dissolve, or open the capsules. Do NOT cut, crush, or chew the tablets.

Patients with CRPC or mCSPC receiving XTANDI should also receive a gonadotropic-releasing hormone (GnRH) analog concurrently or should have had bilateral orchiectomy.

Patients with nmCSPC with high-risk BCR may be treated with XTANDI with or without a GnRH analog. For patients who receive XTANDI with or without a GnRH analog, treatment can be suspended if PSA is undetectable (< 0.2 ng/mL) after 36 weeks of therapy. Reinitiate treatment when PSA has increased to ≥ 2.0 ng/mL for patients who had prior radical prostatectomy or ≥ 5.0 ng/mL for patients who had prior primary radiation therapy [see Clinical Studies (14)].

2.2 Dosage Modifications for Adverse Reactions

If a patient experiences a ≥ Grade 3 or an intolerable adverse reaction, withhold XTANDI for one week or until symptoms improve to ≤ Grade 2, then resume at the same or a reduced dose (120 mg or 80 mg) if warranted [see Warnings and Precautions (5.1, 5.2)].

2.3 Dosage Modifications for Drug Interactions

Strong CYP2C8 Inhibitors

Avoid the coadministration of strong CYP2C8 inhibitors. If the coadministration of a strong CYP2C8 inhibitor cannot be avoided, reduce the XTANDI dosage to 80 mg once daily. If the coadministration of the strong inhibitor is discontinued, increase the XTANDI dosage to the dosage used prior to initiation of the strong CYP2C8 inhibitor [see Clinical Pharmacology (12.3)].

Strong CYP3A4 Inducers

Avoid the coadministration of strong CYP3A4 inducers. If the coadministration of a strong CYP3A4 inducer cannot be avoided, increase the XTANDI dosage from 160 mg to 240 mg orally once daily. If the coadministration of the strong CYP3A4 inducer is discontinued, decrease the XTANDI dosage to the dosage used prior to initiation of the strong CYP3A4 inducer [see Clinical Pharmacology (12.3)].

3 DOSAGE FORMS AND STRENGTHS

XTANDI 40 mg capsules are white to off-white oblong soft gelatin capsules imprinted in black ink with ENZ.

XTANDI 40 mg tablets are yellow, round, film-coated and debossed with E 40.

XTANDI 80 mg tablets are yellow, oval, film-coated and debossed with E 80.

4 CONTRAINDICATIONS

None.

5 WARNINGS AND PRECAUTIONS

5.1 Seizure

Seizure occurred in 0.6% of patients receiving XTANDI in eight randomized clinical trials. In these trials, patients with predisposing factors for seizure were generally excluded. Seizure occurred from 13 to 2250 days after initiation of XTANDI. Patients experiencing seizure were permanently discontinued from therapy, and all seizure events resolved.

In a single-arm trial designed to assess the risk of seizure in patients with pre-disposing factors for seizure, 8 of 366 (2.2%) XTANDI-treated patients experienced a seizure. Three of the 8 patients experienced a second seizure during continued treatment with XTANDI after their first seizure resolved. It is unknown whether anti-epileptic medications will prevent seizures with XTANDI. Patients in the study had one or more of the following pre-disposing factors: the use of medications that may lower the seizure threshold (~ 54%), history of traumatic brain or head injury (~ 28%), history of cerebrovascular accident or transient ischemic attack (~ 24%), and Alzheimer’s disease, meningioma, or leptomeningeal disease from prostate cancer, unexplained loss of consciousness within the last 12 months, past history of seizure, presence of a space occupying lesion of the brain, history of arteriovenous malformation, or history of brain infection (all < 5%). Approximately 17% of patients had more than one risk factor.

Advise patients of the risk of developing a seizure while receiving XTANDI and of engaging in any activity where sudden loss of consciousness could cause serious harm to themselves or others.

Permanently discontinue XTANDI in patients who develop a seizure during treatment.

5.2 Posterior Reversible Encephalopathy Syndrome (PRES)

There have been reports of posterior reversible encephalopathy syndrome (PRES) in patients receiving XTANDI [see Adverse Reactions (6.2)]. PRES is a neurological disorder which can present with rapidly evolving symptoms including seizure, headache, lethargy, confusion, blindness, and other visual and neurological disturbances, with or without associated hypertension. A diagnosis of PRES requires confirmation by brain imaging, preferably magnetic resonance imaging (MRI). Discontinue XTANDI in patients who develop PRES.

5.3 Hypersensitivity

Hypersensitivity reactions, including edema of the face (0.5%), tongue (0.1%), or lip (0.1%) have been observed with enzalutamide in eight randomized clinical trials. Pharyngeal edema has been reported in post-marketing cases. Advise patients who experience any symptoms of hypersensitivity to temporarily discontinue XTANDI and promptly seek medical care. Permanently discontinue XTANDI for serious hypersensitivity reactions.

5.4 Ischemic Heart Disease

In the combined data of five randomized, placebo-controlled clinical studies, ischemic heart disease occurred more commonly in patients on the XTANDI arm compared to patients on the placebo arm (3.5% vs 2%). Grade 3-4 ischemic events occurred in 1.8% of patients on the XTANDI arm compared to 1.1% on the placebo arm. Ischemic events led to death in 0.4% of patients on the XTANDI arm compared to 0.1% on the placebo arm.

Monitor for signs and symptoms of ischemic heart disease. Optimize management of cardiovascular risk factors, such as hypertension, diabetes, or dyslipidemia. Discontinue XTANDI for Grade 3-4 ischemic heart disease.

5.5 Falls and Fractures

Falls and fractures occurred in patients receiving XTANDI. Evaluate patients for fracture and fall risk. Monitor and manage patients at risk for fractures according to established treatment guidelines and consider use of bone-targeted agents.

In the combined data of five randomized, placebo-controlled clinical studies, falls occurred in 12% of patients treated with XTANDI compared to 6% of patients treated with placebo. Falls were not associated with loss of consciousness or seizure. Fractures occurred in 13% of patients treated with XTANDI and in 6% of patients treated with placebo. Grade 3-4 fractures occurred in 3.4% of patients treated with XTANDI and in 1.9% of patients treated with placebo. The median time to onset of fracture was 420 days (range: 1 to 2348 days) for patients treated with XTANDI. Routine bone density assessment and treatment of osteoporosis with bone-targeted agents were not performed in the studies.

5.6 Embryo-Fetal Toxicity

The safety and efficacy of XTANDI have not been established in females. Based on animal reproductive studies and mechanism of action, XTANDI can cause fetal harm and loss of pregnancy when administered to a pregnant female. Advise males with female partners of reproductive potential to use effective contraception during treatment with XTANDI and for 3 months after the last dose of XTANDI [see Use in Specific Populations (8.1, 8.3)].

5.7 Dysphagia or Choking

Severe dysphagia or choking, including events that could be life-threatening requiring medical intervention or fatal, can occur due to XTANDI product size. Advise patients to take each capsule or tablet whole with a sufficient amount of water to ensure that all medication is successfully swallowed. Consider use of a smaller tablet size of XTANDI in patients who have difficulty swallowing. Discontinue XTANDI for patients who cannot swallow capsules or tablets.

5.8 Interference with Immunoassay Measurement of Digoxin:

XTANDI can interfere with certain digoxin immunoassays (e.g., Chemiluminescent Microparticle Immunoassays), resulting in falsely elevated digoxin plasma concentration results. Notify the laboratory conducting the digoxin plasma concentration assay to use an appropriate method in patients receiving XTANDI and digoxin [see Drug Interactions (7.3)].

6 ADVERSE REACTIONS

The following is discussed in more detail in other sections of the labeling:

- Seizure [see Warnings and Precautions (5.1)]
- Posterior Reversible Encephalopathy Syndrome (PRES) [see Warnings and Precautions (5.2)]
- Hypersensitivity [see Warnings and Precautions (5.3)]
- Ischemic Heart Disease [see Warnings and Precautions (5.4)]
- Falls and Fractures [see Warnings and Precautions (5.5)]
- Dysphagia or Choking [see Warnings and Precautions (5.7)]

6.1 Clinical Trial Experience

Because clinical trials are conducted under widely varying conditions, adverse reaction rates observed in the clinical trials of a drug cannot be directly compared to rates in the clinical trials of another drug and may not reflect the rates observed in practice.

The data in WARNINGS and PRECAUTIONS reflect eight randomized, controlled trials [AFFIRM, PREVAIL, TERRAIN, PROSPER, ARCHES, EMBARK, Asian PREVAIL (NCT02294461), and STRIVE (NCT01664923)] that were pooled to conduct safety analyses in patients with CRPC (N = 3651), mCSPC (N = 752), or nmCSPC with high‑risk BCR (N = 707) treated with XTANDI. Patients received XTANDI 160 mg (N = 5110) or placebo orally once daily (N = 2829) or bicalutamide 50 mg orally once daily (N = 387). In these eight trials, the median duration of treatment was 22.1 months (range: < 0.1 to 95.0) in patients that received XTANDI.

In five placebo-controlled trials (AFFIRM, PROSPER, PREVAIL, ARCHES, and EMBARK), the median duration of treatment was 19.4 months (range: < 0.1 to 90.4) in the XTANDI group [see Clinical Studies (14)]. In these five trials, the most common adverse reactions (≥ 10%) that occurred more frequently (≥ 2% over placebo) in the XTANDI-treated patients were musculoskeletal pain, fatigue, hot flush, constipation, decreased appetite, diarrhea, hypertension, hemorrhage, fall, fracture and headache.

AFFIRM: XTANDI versus Placebo in Metastatic CRPC Following Chemotherapy

AFFIRM enrolled 1199 patients with metastatic CRPC who had previously received docetaxel. The median duration of treatment was 8.3 months with XTANDI and 3.0 months with placebo. During the trial, 48% of patients on the XTANDI arm and 46% of patients on the placebo arm received glucocorticoids.

Grade 3 and higher adverse reactions were reported among 47% of XTANDI-treated patients. Discontinuations due to adverse reactions were reported for 16% of XTANDI-treated patients. The most common adverse reaction leading to treatment discontinuation was seizure, which occurred in 0.9% of the XTANDI-treated patients compared to none (0%) of the placebo-treated patients. Table 1 shows adverse reactions reported in AFFIRM that occurred at a ≥ 2% higher frequency in the XTANDI arm compared to the placebo arm.

Table 1. Adverse Reactions in AFFIRM
 | XTANDI (N = 800) |  | Placebo (N = 399)
 | Grade 1-4 [CTCAE v 4.] (%) | Grade 3-4 (%) | Grade 1-4 (%) | Grade 3-4 (%)
General Disorders
Asthenic Conditions [Includes asthenia and fatigue.] | 51 | 9 | 44 | 9
Peripheral Edema | 15 | 1 | 13 | 0.8
Musculoskeletal and Connective Tissue Disorders
Back Pain | 26 | 5 | 24 | 4
Arthralgia | 21 | 2.5 | 17 | 1.8
Musculoskeletal Pain | 15 | 1.3 | 12 | 0.3
Muscular Weakness | 10 | 1.5 | 7 | 1.8
Musculoskeletal Stiffness | 2.6 | 0.3 | 0.3 | 0
Gastrointestinal Disorders
Diarrhea | 22 | 1.1 | 18 | 0.3
Vascular Disorders
Hot Flush | 20 | 0 | 10 | 0
Hypertension | 6 | 2.1 | 2.8 | 1.3
Nervous System Disorders
Headache | 12 | 0.9 | 5 | 0
Dizziness [Includes dizziness and vertigo.] | 9 | 0.5 | 7 | 0.5
Spinal Cord Compression and Cauda Equina Syndrome | 7 | 7 | 4.5 | 3.8
Paresthesia | 7 | 0 | 4.5 | 0
Mental Impairment Disorders [Includes amnesia, memory impairment, cognitive disorder, and disturbance in attention.] | 4.3 | 0.3 | 1.8 | 0
Hypoesthesia | 4 | 0.3 | 1.8 | 0
Infections and Infestations
Upper Respiratory Tract Infection [Includes nasopharyngitis, upper respiratory tract infection, sinusitis, rhinitis, pharyngitis, and laryngitis.] | 11 | 0 | 6 | 0.3
Lower Respiratory Tract And Lung Infection [Includes pneumonia, lower respiratory tract infection, bronchitis, and lung infection.] | 8 | 2.4 | 4.8 | 1.3
Psychiatric Disorders
Insomnia | 9 | 0 | 6 | 0.5
Anxiety | 6 | 0.3 | 4 | 0
Renal and Urinary Disorders
Hematuria | 7 | 1.8 | 4.5 | 1
Pollakiuria | 4.8 | 0 | 2.5 | 0
Injury, Poisoning and Procedural Complications
Fall | 4.6 | 0.3 | 1.3 | 0
Non-pathologic Fractures | 4 | 1.4 | 0.8 | 0.3
Skin and Subcutaneous Tissue Disorders
Pruritus | 3.8 | 0 | 1.3 | 0
Dry Skin | 3.5 | 0 | 1.3 | 0
Respiratory Disorders
Epistaxis | 3.3 | 0.1 | 1.3 | 0.3

PREVAIL: XTANDI versus Placebo in Chemotherapy-naïve Metastatic CRPC

PREVAIL enrolled 1717 patients with metastatic CRPC who had not received prior cytotoxic chemotherapy, of whom 1715 received at least one dose of study drug. The median duration of treatment was 17.5 months with XTANDI and 4.6 months with placebo. Grade 3-4 adverse reactions were reported in 44% of XTANDI-treated patients and 37% of placebo-treated patients. Discontinuations due to adverse reactions were reported for 6% of XTANDI-treated patients. The most common adverse reaction leading to treatment discontinuation was fatigue/asthenia, which occurred in 1% of patients on each treatment arm. Table 2 includes adverse reactions reported in PREVAIL that occurred at a ≥ 2% higher frequency in the XTANDI arm compared to the placebo arm.

Table 2. Adverse Reactions in PREVAIL
 | XTANDI (N = 871) |  | Placebo (N = 844)
 | Grade 1-4 [CTCAE v 4.] (%) | Grade 3-4 (%) | Grade 1-4 (%) | Grade 3-4 (%)
General Disorders
Asthenic Conditions [Includes asthenia and fatigue.] | 47 | 3.4 | 33 | 2.8
Peripheral Edema | 12 | 0.2 | 8 | 0.4
Musculoskeletal and Connective Tissue Disorders
Back Pain | 29 | 2 | 22 | 3
Arthralgia | 21 | 1.6 | 16 | 1.1
Gastrointestinal Disorders
Constipation | 23 | 0.7 | 17 | 0.4
Diarrhea | 17 | 0.3 | 14 | 0.4
Vascular Disorders
Hot Flush | 18 | 0.1 | 8 | 0
Hypertension | 14 | 7 | 4.1 | 2.3
Nervous System Disorders
Dizziness [Includes dizziness and vertigo.] | 11 | 0.3 | 7 | 0
Headache | 11 | 0.2 | 7 | 0.4
Dysgeusia | 8 | 0.1 | 3.7 | 0
Mental Impairment Disorders [Includes amnesia, memory impairment, cognitive disorder, and disturbance in attention.] | 6 | 0 | 1.3 | 0.1
Restless Legs Syndrome | 2.1 | 0.1 | 0.4 | 0
Respiratory Disorders
Dyspnea [Includes dyspnea, exertional dyspnea, and dyspnea at rest.] | 11 | 0.6 | 8 | 0.6
Infections and Infestations
Upper Respiratory Tract Infection [Includes nasopharyngitis, upper respiratory tract infection, sinusitis, rhinitis, pharyngitis, and laryngitis.] | 16 | 0 | 11 | 0
Lower Respiratory Tract And Lung Infection [Includes pneumonia, lower respiratory tract infection, bronchitis, and lung infection.] | 8 | 1.5 | 4.7 | 1.1
Psychiatric Disorders
Insomnia | 8 | 0.1 | 6 | 0
Renal and Urinary Disorders
Hematuria | 9 | 1.3 | 6 | 1.3
Injury, Poisoning and Procedural Complications
Fall | 13 | 1.6 | 5 | 0.7
Non-Pathological Fracture | 9 | 2.1 | 3 | 1.1
Metabolism and Nutrition Disorders
Decreased Appetite | 19 | 0.3 | 16 | 0.7
Investigations
Weight Decreased | 12 | 0.8 | 8 | 0.2
Reproductive System and Breast Disorders
Gynecomastia | 3.4 | 0 | 1.4 | 0

TERRAIN: XTANDI versus Bicalutamide in Chemotherapy-naïve Metastatic CRPC

TERRAIN enrolled 375 patients with metastatic CRPC who had not received prior cytotoxic chemotherapy, of whom 372 received at least one dose of study drug. The median duration of treatment was 11.6 months with XTANDI and 5.8 months with bicalutamide. Discontinuations with an adverse reaction as the primary reason were reported for 8% of XTANDI-treated patients and 6% of bicalutamide-treated patients. The most common adverse reactions leading to treatment discontinuation were back pain and pathological fracture, which occurred in 3.8% of XTANDI-treated patients for each event and in 2.1% and 1.6% of bicalutamide-treated patients, respectively. Table 3 shows overall and common adverse reactions (≥ 10%) in XTANDI-treated patients.

Table 3. Adverse Reactions in TERRAIN
 | XTANDI (N = 183) |  | Bicalutamide (N = 189)
 | Grade 1-4 [CTCAE v 4.] (%) | Grade 3-4 (%) | Grade 1-4 (%) | Grade 3-4 (%)
Overall | 94 | 39 | 94 | 38
General Disorders
Asthenic Conditions [Including asthenia and fatigue.] | 32 | 1.6 | 23 | 1.1
Musculoskeletal and Connective Tissue Disorders
Back Pain | 19 | 2.7 | 18 | 1.6
Musculoskeletal Pain [Including musculoskeletal pain and pain in extremity.] | 16 | 1.1 | 14 | 0.5
Vascular Disorders
Hot Flush | 15 | 0 | 11 | 0
Hypertension | 14 | 7 | 7 | 4.2
Gastrointestinal Disorders
Nausea | 14 | 0 | 18 | 0
Constipation | 13 | 1.1 | 13 | 0.5
Diarrhea | 12 | 0 | 9 | 1.1
Infections and Infestations
Upper Respiratory Tract Infection [Including nasopharyngitis, upper respiratory tract infection, sinusitis, rhinitis, pharyngitis, and laryngitis.] | 12 | 0 | 6 | 0.5
Investigational
Weight Loss | 11 | 0.5 | 8 | 0.5

PROSPER: XTANDI versus Placebo in Non-metastatic CRPC Patients

PROSPER enrolled 1401 patients with non-metastatic CRPC, of whom 1395 received at least one dose of study drug. Patients were randomized 2:1 and received either XTANDI at a dose of 160 mg once daily (N = 930) or placebo (N = 465). The median duration of treatment at the time of analysis was 18.4 months (range: 0.0 to 42 months) with XTANDI and 11.1 months (range: 0.0 to 43 months) with placebo.

Overall, 32 patients (3.4%) receiving XTANDI died from adverse reactions. The reasons for death with ≥ 2 patients included coronary artery disorders (n = 7), sudden death (n = 2), cardiac arrhythmias (n = 2), general physical health deterioration (n = 2), stroke (n = 2), and secondary malignancy (n = 5; one each of acute myeloid leukemia, brain neoplasm, mesothelioma, small cell lung cancer, and malignant neoplasm of unknown primary site). Three patients (0.6%) receiving placebo died from adverse reactions of cardiac arrest (n = 1), left ventricular failure (n = 1), and pancreatic carcinoma (n = 1). Grade 3 or higher adverse reactions were reported among 31% of XTANDI-treated patients and 23% of placebo‑treated patients. Discontinuations with an adverse reaction as the primary reason were reported for 9% of XTANDI-treated patients and 6% of placebo-treated patients. Of these, the most common adverse reaction leading to treatment discontinuation was fatigue, which occurred in 1.6% of the XTANDI-treated patients compared to none of the placebo-treated patients. Table 4 shows adverse reactions reported in PROSPER that occurred at a ≥ 2% higher frequency in the XTANDI arm than in the placebo arm.

Table 4. Adverse Reactions in PROSPER
 | XTANDI (N = 930) |  | Placebo (N = 465)
 | Grade 1-4 [CTCAE v 4.] (%) | Grade 3-4 (%) | Grade 1-4 (%) | Grade 3-4 (%)
Metabolism and Nutrition Disorders
Decreased Appetite | 10 | 0.2 | 3.9 | 0.2
Nervous System Disorders
Dizziness [Includes dizziness and vertigo.] | 12 | 0.5 | 5 | 0
Headache | 9 | 0.2 | 4.5 | 0
Cognitive and Attention Disorders [Includes amnesia, memory impairment, cognitive disorder, and disturbance in attention.] | 4.6 | 0.1 | 1.5 | 0
Vascular Disorders
Hot Flush | 13 | 0.1 | 8 | 0
Hypertension | 12 | 4.6 | 5 | 2.2
Gastrointestinal Disorders
Nausea | 11 | 0.3 | 9 | 0
Constipation | 9 | 0.2 | 7 | 0.4
General Disorders and Administration Site Conditions
Asthenic Conditions [Includes asthenia and fatigue.] | 40 | 4 | 20 | 0.9
Investigations
Weight Decreased | 6 | 0.2 | 1.5 | 0
Injury, Poisoning and Procedural Complications
Fall | 11 | 1.3 | 4.1 | 0.6
Fractures [Includes all osseous fractures from all sites.] | 10 | 2 | 4.9 | 1.7
Psychiatric Disorders
Anxiety | 2.8 | 0.2 | 0.4 | 0

ARCHES: XTANDI versus Placebo in Metastatic CSPC Patients

ARCHES randomized 1150 patients with mCSPC, of whom 1146 received at least one dose of study drug. All patients received either a gonadotropin-releasing hormone (GnRH) analog concurrently or had bilateral orchiectomy. Patients received either XTANDI at a dose of 160 mg once daily (N = 572) or placebo (N = 574). The median duration of treatment was 12.8 months (range: 0.2 to 26.6 months) with XTANDI and 11.6 months (range: 0.2 to 24.6 months) with placebo.

Overall, 10 patients (1.7%) receiving XTANDI died from adverse reactions. The reasons for death in ≥ 2 patients included heart disease (n = 3), sepsis (n = 2) and pulmonary embolism (n = 2). Eight patients (1.4%) receiving placebo died from adverse reactions. The reasons for death in ≥ 2 patients included heart disease (n = 2) and sudden death (n = 2). Grade 3 or higher adverse reactions were reported in 24% of patients treated with XTANDI. Permanent discontinuation due to adverse reactions as the primary reason was reported in 4.9% of XTANDI-treated patients and 3.7% of placebo-treated patients. The most common adverse reactions resulting in permanent discontinuation in XTANDI-treated patients were alanine aminotransferase increased, aspartate aminotransferase elevation, and seizure, each in 0.3%. The most common adverse reactions leading to permanent discontinuation in placebo-treated patients were arthralgia, and fatigue, each in 0.3%.

Dose reductions due to an adverse reaction occurred in 4.4% of patients who received XTANDI. Fatigue/asthenia was the most frequent adverse reaction requiring dose reduction in 2.1% of XTANDI-treated patients and 0.7% of placebo-treated patients.

Table 5 shows adverse reactions reported in ARCHES that occurred at a ≥ 2% higher frequency in the XTANDI arm than in the placebo arm.

Table 5. Adverse Reactions in ARCHES
 | XTANDI (N = 572) |  | Placebo (N = 574)
 | Grade 1-4 [CTCAE v 4.03.] (%) | Grade 3-4 (%) | Grade 1-4 (%) | Grade 3-4 (%)
Metabolism and Nutrition Disorders
Decreased Appetite | 4.9 | 0.2 | 2.6 | 0
Nervous System Disorders
Cognitive and Memory Impairment [Includes memory impairment, amnesia, cognitive disorder, dementia, disturbance in attention, transient global amnesia, dementia alzheimer’s type, mental impairment, senile dementia and vascular dementia.] | 4.5 | 0.7 | 2.1 | 0
Restless Legs Syndrome | 2.4 | 0 | 0.3 | 0
Vascular Disorders
Hot Flush | 27 | 0.3 | 22 | 0
Hypertension | 8 | 3.3 | 6 | 1.7
General Disorders and Administration Site Conditions
Asthenic conditions [Includes asthenia and fatigue.] | 24 | 1.7 | 20 | 1.6
Musculoskeletal and Connective Tissue Disorders
Musculoskeletal Pain | 6 | 0.2 | 4 | 0.2
Injury, Poisoning and Procedural Complications
Fractures [Includes Fracture related preferred terms under high level terms: fractures NEC; fractures and dislocations NEC; limb fractures and dislocations; pelvic fractures and dislocations; skull and brain therapeutic procedures; skull fractures, facial bone fractures and dislocations; spinal fractures and dislocations; thoracic cage fractures and dislocations.] | 6 | 1.0 | 4.2 | 1

EMBARK: XTANDI versus Placebo in Non-metastatic CSPC Patients with High-Risk BCR

EMBARK enrolled 1068 patients with high-risk BCR, of whom 1061 patients received at least one dose of study drug. Patients received XTANDI at a dose of 160 mg once daily concurrently with leuprolide (N = 353), XTANDI at a dose of 160 mg once daily as open‑label monotherapy (N = 354), or placebo concurrently with leuprolide (N = 354). At week 37, treatment was suspended for patients whose PSA values were undetectable (<0.2 ng/mL) at week 36. Treatment was reinitiated when PSA values increased to ≥2.0 ng/mL for patients with prior prostatectomy or ≥5.0 ng/mL for patients without prior prostatectomy. For patients whose PSA values were detectable (≥0.2 ng/mL) at week 36, treatment continued without suspension until permanent treatment discontinuation criteria were met.

Table 6 shows the total duration of treatment for the three treatment arms.

Table 6. Drug Treatment and Suspension in EMBARK
 | XTANDI + Leuprolide (N = 353) | Placebo + Leuprolide (N = 354) | XTANDI (N = 354)
Total Duration of Treatment [Inclusive of time receiving drug treatment plus any time during which drug treatment was suspended because of undetectable PSA levels.]
Median, months | 60.6 | 55.6 | 60.4
Range, months | 0.1 - 90.4 | 0.7 - 94.1 | 0.4 – 95.0
Duration Receiving Drug Treatment
Median, months | 32.4 | 35.4 | 45.9
Range, months | 0.1 – 83.4 | 0.7 – 85.7 | 0.4 – 88.9
Duration of Suspension from Drug Treatment
Median, months | 18.0 | 16.6 | 9.4
Range, months | 1.4 – 87.9 | 3.4 – 83.0 | 2.0 – 77.7
Patients who had Drug Treatment Suspended at Week 37
Number of Patients (%) | 321 (90.9) | 240 (67.8) | 304 (85.9)

Overall, deaths from adverse reactions during the total duration of treatment occurred in 6 patients (1.7%) receiving XTANDI plus leuprolide, 8 patients (2.3%) receiving XTANDI as a single agent, and 3 patients (0.8%) receiving placebo plus leuprolide. The reason for death in ≥ 2 patients receiving XTANDI plus leuprolide was infection (n = 2), and the reason for death in ≥ 2 patients receiving XTANDI as a single agent was arterial thromboembolism (n=2).

Grade 3 or higher adverse reactions during the total duration of treatment were reported in 46% of patients treated with XTANDI plus leuprolide, 50% of patients receiving XTANDI as a single agent, and 43% of patients receiving placebo plus leuprolide. Permanent treatment discontinuation due to adverse reactions during the total duration of treatment as the primary reason was reported in 21% of patients treated with XTANDI plus leuprolide, 18% of patients receiving XTANDI as a single agent, and 10% of patients receiving placebo plus leuprolide. The most common adverse reactions resulting in permanent discontinuation included fatigue (3.4% of patients treated with XTANDI plus leuprolide, 3.7% of patients receiving XTANDI as a single agent, and 1.4% of patients receiving placebo plus leuprolide), hot flush (2% of patients treated with XTANDI plus leuprolide, 0% of patients receiving XTANDI as a single agent, and 1.1% of patients receiving placebo plus leuprolide), nausea (1.1% of patients treated with XTANDI plus leuprolide, 0.6% of patients receiving XTANDI as a single agent, and 0.3% of patients receiving placebo plus leuprolide), and cognitive disorder (1.1% of patients treated with XTANDI plus leuprolide, 1.4% of patients receiving XTANDI as a single agent, and 0.8% of patients receiving placebo plus leuprolide).

Dose reductions due to an adverse reaction occurred in 7% of patients who received XTANDI plus leuprolide, 16% of patients who received XTANDI as a single agent, and 4.5% of patients who received placebo plus leuprolide. Fatigue was the most frequent adverse reaction requiring dose reduction in 3.1% of patients treated with XTANDI plus leuprolide, 10% of patients receiving XTANDI as a single agent, and 1.7% of patients receiving placebo plus leuprolide.

Table 7 shows adverse reactions reported in EMBARK that occurred at a ≥ 5% (Grade 1-4) or ≥ 2% (Grade 3-4) higher frequency in either of the XTANDI arms than in the placebo arm.

Table 7. Adverse Reactions in EMBARK
 | XTANDI + Leuprolide (N = 353) |  | Placebo + Leuprolide (N = 354) |  | XTANDI (N = 354)
 | Grade 1-4 [CTCAE v 4.03.] (%) | Grade 3-4 (%) | Grade 1-4 (%) | Grade 3‑4 (%) | Grade 1-4 (%) | Grade 3-4 (%)
Nervous System Disorders
Cognitive Disorder [Includes multiple terms.] | 10 | 0.3 | 4.8 | 0.6 | 10 | 0.3
Syncope | 4.8 | 4.2 | 2.3 | 1.7 | 2.5 | 2
Vascular Disorders
Hot Flush | 69 | 0.6 | 57 | 0.8 | 22 | 0.3
Hemorrhage | 20 | 3.4 | 15 | 1.7 | 21 | 3.7
Gastrointestinal Disorders
Diarrhea | 15 | 0.6 | 9 | 0.8 | 14 | 0.3
Nausea | 12 | 0.3 | 8 | 0.3 | 15 | 0.6
Investigations
Weight Decreased | 7 | 0.3 | 3.4 | 0 | 11 | 0.3
General Disorders and Administration Site Conditions
Fatigue | 50 | 4 | 38 | 1.7 | 54 | 4.8
Musculoskeletal and Connective Tissue Disorders
Musculoskeletal Pain | 50 | 4.8 | 43 | 2.3 | 48 | 3.1
Osteoarthritis | 6 | 2.8 | 4.2 | 0.6 | 5 | 0.6
Injury, Poisoning and Procedural Complications
Fall | 21 | 1.1 | 14 | 1.1 | 16 | 2
Fracture | 18 | 4 | 13 | 2.5 | 11 | 2
Reproductive System and Breast Disorders
Gynecomastia | 9 | 0 | 10 | 0 | 49 | 0.8
Breast tenderness | 5 | 0 | 2.8 | 0 | 35 | 0
Cardiac Disorders
Ischemic Heart Disease | 5 | 4 | 6 | 3.1 | 9 | 6

Clinically relevant adverse reactions that did not meet criteria for inclusion in Table 7 include hypertension (XTANDI plus leuprolide, 25%; XTANDI as a single agent, 21%), angioedema (XTANDI plus leuprolide, 2.5%; XTANDI as a single agent, 2%), and seizure (XTANDI plus leuprolide, 1.1%; XTANDI as a single agent, 0.8%).

Laboratory Abnormalities

Table 8 shows laboratory abnormalities that occurred in ≥ 5% of patients, and more frequently (> 2%) in the XTANDI arm compared to placebo in the pooled, randomized, placebo-controlled studies.

Table 8. Laboratory Abnormalities
 | XTANDI (N = 3526) |  | Placebo (N = 2636)
 | Grade 1-4 (%) | Grade 3-4 (%) | Grade 1-4 (%) | Grade 3-4 (%)
Hematology
Hemoglobin decreased | 50 | 1.8 | 47 | 1.5
Neutrophil count decreased | 20 | 1 | 17 | 0.5
White blood cell decreased | 18 | 0.5 | 11 | 0.2
Chemistry
Hyperglycemia | 86 | 3.7 | 78 | 4.3
Hypermagnesemia | 17 | 0.1 | 14 | 0.3
Hyponatremia | 14 | 1.6 | 9 | 1.4
Hypophosphatemia | 10 | 1.4 | 7 | 0.8
Hypercalcemia | 8 | 0.1 | 5 | 0.1

Hypertension

In the combined data from five randomized placebo-controlled clinical trials, hypertension was reported in 14% of patients receiving XTANDI and 7% of patients receiving placebo. Medical history of hypertension was balanced between arms. Hypertension led to study discontinuation in < 1% of patients in each arm.

6.2 Post-Marketing Experience

The following additional adverse reactions have been identified during post-approval use of XTANDI. Because these reactions are reported voluntarily from a population of uncertain size, it is not always possible to reliably estimate their frequency or establish a causal relationship to drug exposure.

Gastrointestinal Disorders: vomiting, dysphagia (including choking related to XTANDI product size)

Immune System Disorders: hypersensitivity (edema of the face, tongue, lip, or pharynx)

Neurological Disorders: posterior reversible encephalopathy syndrome (PRES), dysgeusia

Skin and Subcutaneous Tissue Disorders: rash, severe cutaneous adverse reactions (including Stevens-Johnson syndrome (SJS), erythema multiforme, toxic epidermal necrolysis (TEN), drug reaction with eosinophilia and systemic symptoms (DRESS) and acute generalized exanthematous pustulosis (AGEP))

7 DRUG INTERACTIONS

7.1 Effect of Other Drugs on XTANDI

Strong CYP2C8 Inhibitors

The coadministration of XTANDI with gemfibrozil (a strong CYP2C8 inhibitor) increases plasma concentrations of enzalutamide plus N-desmethyl enzalutamide, which may increase the incidence and severity of adverse reactions of XTANDI. Avoid the coadministration of XTANDI with strong CYP2C8 inhibitors. If the coadministration of XTANDI with a strong CYP2C8 inhibitor cannot be avoided, reduce the dosage of XTANDI [see Dosage and Administration (2.3), Clinical Pharmacology (12.3)].

Strong CYP3A4 Inducers

The coadministration of XTANDI with rifampin (a strong CYP3A4 inducer and a moderate CYP2C8 inducer) decreases plasma concentrations of enzalutamide plus N-desmethyl enzalutamide, which may decrease the efficacy of XTANDI. Avoid the coadministration of XTANDI with strong CYP3A4 inducers. If the coadministration of XTANDI with a strong CYP3A4 inducer cannot be avoided, increase the dosage of XTANDI [see Dosage and Administration (2.3), Clinical Pharmacology (12.3)].

7.2 Effect of XTANDI on Other Drugs

Certain CYP3A4, CYP2C9, or CYP2C19 Substrates

XTANDI is a strong CYP3A4 inducer and a moderate CYP2C9 and CYP2C19 inducer. The coadministration of XTANDI decreases the concentrations of certain CYP3A4, CYP2C9, or CYP2C19 substrates [see Clinical Pharmacology (12.3)], which may reduce the efficacy of these substrates. Avoid the coadministration of XTANDI with certain CYP3A4, CYP2C9, or CYP2C19 substrates for which a minimal decrease in concentration may lead to therapeutic failure of the substrate. If the coadministration cannot be avoided, increase the dosage of these substrates in accordance with their Prescribing Information. In cases where active metabolites are formed, there may be increased exposure to the active metabolites.

7.3 Laboratory Test Interference

XTANDI can interfere with certain digoxin immunoassays (e.g., Chemiluminescent Microparticle Immunoassays), resulting in falsely elevated digoxin plasma concentration results. Notify the laboratory conducting the digoxin plasma concentration assay to use an appropriate method in patients receiving XTANDI and digoxin [see Warnings and Precautions (5.8)].

8 USE IN SPECIFIC POPULATIONS

8.1 Pregnancy

Risk Summary

The safety and efficacy of XTANDI have not been established in females. Based on animal reproductive studies and mechanism of action, XTANDI can cause fetal harm and loss of pregnancy. There are no human data on the use of XTANDI in pregnant females. In animal reproduction studies, oral administration of enzalutamide in pregnant mice during organogenesis caused adverse developmental effects at doses lower than the maximum recommended human dose (see Data).

Data

Animal Data

In an embryo-fetal developmental toxicity study in mice, enzalutamide caused developmental toxicity when administered at oral doses of 10 or 30 mg/kg/day throughout the period of organogenesis (gestational days 6-15). Findings included embryo-fetal lethality (increased post-implantation loss and resorptions) and decreased anogenital distance at ≥ 10 mg/kg/day, and cleft palate and absent palatine bone at 30 mg/kg/day. Doses of 30 mg/kg/day caused maternal toxicity. The doses tested in mice (1, 10 and 30 mg/kg/day) resulted in systemic exposures (AUC) approximately 0.04, 0.4 and 1.1 times, respectively, the exposures in patients. Enzalutamide did not cause developmental toxicity in rabbits when administered throughout the period of organogenesis (gestational days 6-18) at dose levels up to 10 mg/kg/day (approximately 0.4 times the exposures in patients based on AUC).

In a pharmacokinetic study in pregnant rats with a single oral 30 mg/kg enzalutamide administration on gestation day 14, enzalutamide and/or its metabolites were present in the fetus at a Cmax that was approximately 0.3 times the concentration found in maternal plasma and occurred 4 hours after administration.

8.2 Lactation

Risk Summary

The safety and efficacy of XTANDI have not been established in females. There is no information available on the presence of XTANDI in human milk, the effects of the drug on the breastfed infant, or the effects of the drug on milk production. Enzalutamide and/or its metabolites were present in milk of lactating rats (see Data).

Data

Following a single oral administration in lactating rats on postnatal day 14, enzalutamide and/or its metabolites were present in milk at a Cmax that was 4 times higher than concentrations in the plasma and occurred 4 hours after administration.

8.3 Females and Males of Reproductive Potential

Contraception

Males

Based on findings in animal reproduction studies, advise male patients with female partners of reproductive potential to use effective contraception during treatment and for 3 months after the last dose of XTANDI [see Use in Specific Populations (8.1)].

Infertility

Males

Based on animal studies, XTANDI may impair fertility in males of reproductive potential [see Nonclinical Toxicology (13.1)].

8.4 Pediatric Use

Safety and effectiveness of XTANDI in pediatric patients have not been established.

8.5 Geriatric Use

Of 5110 patients who received XTANDI in eight randomized, controlled clinical trials, 78% were 65 and over, while 33% were 75 and over. No overall differences in safety or effectiveness were observed between these patients and younger patients. Other reported clinical experience has not identified differences in responses between the elderly and younger patients, but greater sensitivity of some older individuals cannot be ruled out.

8.6 Renal Impairment

No dosage modification is recommended for patients with mild to moderate renal impairment (creatinine clearance [CLcr] ≥ 30 mL/min). XTANDI has not been studied in patients with severe renal impairment (CLcr < 30 mL/min) or end-stage renal disease [see Clinical Pharmacology (12.3)].

8.7 Hepatic Impairment

No dosage modification is recommended for patients with mild, moderate, or severe hepatic impairment [see Clinical Pharmacology (12.3)].

10 OVERDOSAGE

In the event of an overdosage, stop treatment with XTANDI and initiate general supportive measures taking into consideration the half-life of 5.8 days. In a dose escalation study, no seizures were reported at < 240 mg daily, whereas 3 seizures were reported, 1 each at 360 mg, 480 mg, and 600 mg daily. Patients may be at increased risk of seizure following an overdosage.

11 DESCRIPTION

Enzalutamide is an androgen receptor inhibitor. The chemical name is 4-{3-[4-cyano-3-(trifluoromethyl)phenyl]-5,5-dimethyl-4-oxo-2-sulfanylideneimidazolidin-1-yl}-2-fluoro-N-methylbenzamide.

The molecular weight is 464.44 and molecular formula is C21H16F4N4O2S. The structural formula is:

Enzalutamide is a white crystalline non-hygroscopic solid. It is practically insoluble in water.

XTANDI is available as liquid-filled soft gelatin capsules for oral administration. Each capsule contains 40 mg of enzalutamide as a solution in caprylocaproyl polyoxylglycerides. The inactive ingredients are caprylocaproyl polyoxylglycerides, butylated hydroxyanisole, butylated hydroxytoluene, gelatin, sorbitol sorbitan solution, glycerin, purified water, titanium dioxide, and black iron oxide.

XTANDI is also available as film-coated tablets for oral administration. Each tablet contains 40 mg or 80 mg of enzalutamide. The inactive ingredients are hypromellose acetate succinate, microcrystalline cellulose, colloidal silicon dioxide, croscarmellose sodium, and magnesium stearate. The tablet film-coat contains hypromellose, talc, polyethylene glycol, titanium dioxide, and ferric oxide.

12 CLINICAL PHARMACOLOGY

12.1 Mechanism of Action

Enzalutamide is an androgen receptor inhibitor that acts on different steps in the androgen receptor signaling pathway. Enzalutamide has been shown to competitively inhibit androgen binding to androgen receptors; and consequently, inhibits nuclear translocation of androgen receptors and their interaction with DNA. A major metabolite, N‑desmethyl enzalutamide, exhibited similar in vitro activity to enzalutamide. Enzalutamide decreased proliferation and induced cell death of prostate cancer cells in vitro, and decreased tumor volume in a mouse prostate cancer xenograft model.

12.2 Pharmacodynamics

Once daily dosing of 160 mg enzalutamide in addition to ADT reduced PSA levels to undetectable levels (< 0.2 ng/mL) in 68% of patients with mCSPC (ARCHES).

Based on the efficacy results of AFFIRM after once daily dosing of 160 mg enzalutamide, no exposure‑response relationship for the efficacy endpoint of overall survival could be identified. In addition, there was no clinically meaningful exposure-response relationship for adverse effects (e.g. fatigue, flushing, headache, or hypertension) within the limited exposure range for 160 mg/day.

Cardiac Electrophysiology

At the recommended dosage, XTANDI does not cause large mean increases (i.e., > 20 msec) in the QT interval.

12.3 Pharmacokinetics

Enzalutamide achieves steady-state by Day 28 and its AUC accumulates approximately 8.3-fold relative to a single dose. At steady-state, the mean (%CV) maximum concentration (Cmax) for enzalutamide and N-desmethyl enzalutamide are 16.6 µg/mL (23%) and 12.7 µg/mL (30%), respectively, and the mean (%CV) minimum concentrations (Cmin) are 11.4 µg/mL (26%) and 13.0 µg/mL (30%), respectively.

Enzalutamide showed approximately dose proportional pharmacokinetics over the daily dose range of 30 (0.2 times the approved recommended dosage) to 360 mg (2.25 times the approved recommended dosage).

Absorption

The median Tmax is 1 hour (0.5 to 3 hours) following a single 160 mg dose of capsules and 2 hours (0.5 to 6 hours) following a single 160 mg dose of tablets.

Effect of Food

There was no clinically meaningful effect on enzalutamide or N-desmethyl enzalutamide pharmacokinetics following the administration of XTANDI with a high‑fat meal (approximately 150 calories from protein, 250 calories from carbohydrates, and 500 to 600 calories from fat).

Distribution

The mean (%CV) volume of distribution after a single oral dose is 110 L (29%).

Enzalutamide is 97% to 98% bound to plasma proteins, primarily albumin. N-desmethyl enzalutamide is 95% bound to plasma proteins.

Elimination

Enzalutamide is primarily eliminated by hepatic metabolism.

The mean apparent clearance (CL/F) of enzalutamide after a single dose is 0.56 L/h (0.33 to 1.02 L/h). The mean terminal half-life (t1/2) for enzalutamide after a single oral dose is 5.8 days (2.8 to 10.2 days). The mean terminal t1/2 for N‑desmethyl enzalutamide is approximately 7.8 to 8.6 days.

Metabolism

Enzalutamide is metabolized by CYP2C8 and CYP3A4. CYP2C8 is primarily responsible for the formation of the active metabolite (N-desmethyl enzalutamide). Carboxylesterase 1 metabolizes N-desmethyl enzalutamide and enzalutamide to the inactive carboxylic acid metabolite.

Specific Populations

No clinically meaningful differences in the pharmacokinetics of enzalutamide were observed based on age (41 to 92 years), race (White, Chinese, and Japanese), body weight (46 kg to 163 kg), mild to moderate renal impairment (CLcr ≥ 30 mL/min) and hepatic impairment (Child-Pugh A, B, and C). Severe renal impairment and end stage renal disease (CLcr < 30 mL/min) have not been studied.

Drug Interaction Studies

Clinical Studies

Effect of CYP2C8 Inhibitors on XTANDI: The coadministration of XTANDI 160 mg with gemfibrozil (strong CYP2C8 inhibitor) increased the AUC of enzalutamide plus N-desmethyl enzalutamide by 2.2-fold with minimal effect on Cmax.

Effect of CYP3A4 and CYP2C8 Inducers on XTANDI: The coadministration of XTANDI 160 mg after multiple oral doses of rifampin (strong CYP3A4 and moderate CYP2C8 inducer) decreased the AUC of enzalutamide plus N-desmethyl enzalutamide by 37% with no effect on Cmax.

Effect of CYP3A4 Inhibitors on XTANDI: The coadministration of XTANDI 160 mg after multiple oral doses of itraconazole (strong CYP3A4 inhibitor) increased the AUC of enzalutamide plus N-desmethyl enzalutamide by 1.3-fold with no effect on Cmax.

Effect of XTANDI on Other Drugs:

The coadministration of XTANDI 160 mg orally once daily with midazolam (a sensitive CYP3A4 substrate) decreased midazolam AUC by 86% and Cmax by 77%.

Coadministration of XTANDI 160 mg orally once daily with warfarin (a sensitive CYP2C9 substrate) decreased S‑warfarin AUC by 56% and Cmax by 17%.

Coadministration of XTANDI 160 mg orally once daily with omeprazole (a sensitive CYP2C19 substrate) decreased omeprazole AUC by 72% and Cmax by 62%.

Coadministration of XTANDI 160 mg orally once daily with digoxin (a P-glycoprotein substrate) increased digoxin AUC by 33% and Cmax by 17%.

No clinically meaningful changes in exposure of pioglitazone (a sensitive CYP2C8 substrate), caffeine (a sensitive CYP1A2 substrate), dextromethorphan (a sensitive CYP2D6 substrate), or rosuvastatin (a BCRP substrate) were observed following coadministration with XTANDI.

In Vitro Studies

Cytochrome P450 (CYP) Enzymes: Enzalutamide induces CYP2B6 at clinically achievable concentrations.

Transporter Systems: Enzalutamide, N-desmethyl enzalutamide, and the major inactive carboxylic acid metabolite are not substrates for P-glycoprotein or BCRP.

13 NONCLINICAL TOXICOLOGY

13.1 Carcinogenesis, Mutagenesis, Impairment of Fertility

A two-year carcinogenicity study was conducted in male and female rats at oral enzalutamide doses of 10, 30, and 100 mg/kg/day. Enzalutamide increased the incidence of benign Leydig cell tumors in the testes at all dose levels tested (≥ 0.3 times the human exposure based on AUC) and combined incidence of urothelial papilloma and carcinoma in the urinary bladder in male rats at 100 mg/kg/day (1.4 times the human exposure based on AUC). The findings in the testes are considered to be related to the pharmacological activity of enzalutamide. Rats are regarded as more sensitive than humans to developing interstitial cell tumors in the testes. Administration of enzalutamide to male and female rasH2 transgenic mice by oral gavage daily for 26 weeks did not result in increased incidence of neoplasms at doses up to 20 mg/kg/day.

Enzalutamide did not induce mutations in the bacterial reverse mutation (Ames) assay and was not genotoxic in either the in vitro mouse lymphoma thymidine kinase (Tk) gene mutation assay or the in vivo mouse micronucleus assay.

Based on nonclinical findings in repeat-dose toxicology studies, which were consistent with the pharmacological activity of enzalutamide, male fertility may be impaired by treatment with XTANDI. In a 26-week study in rats, atrophy of the prostate and seminal vesicles was observed at ≥ 30 mg/kg/day (equal to the human exposure based on AUC). In 4-, 13-, and 39-week studies in dogs, hypospermatogenesis and atrophy of the prostate and epididymides were observed at ≥ 4 mg/kg/day (0.3 times the human exposure based on AUC).

14 CLINICAL STUDIES

The efficacy of XTANDI in patients with CRPC (N = 4692), mCSPC (N = 1150), or nmCSPC with high‑risk BCR (N = 1068) was demonstrated in six randomized, multicenter clinical trials. Patients received concomitant GnRH therapy or had prior bilateral orchiectomy, unless otherwise indicated.

AFFIRM (NCT00974311): XTANDI versus Placebo in Metastatic CRPC Following Chemotherapy

In AFFIRM, a total of 1199 patients who had received prior docetaxel-based chemotherapy were randomized 2:1 to receive either XTANDI orally at a dose of 160 mg once daily (N = 800) or placebo orally once daily (N = 399). Study treatment continued until disease progression (evidence of radiographic progression, a skeletal-related event, or clinical progression), initiation of new systemic antineoplastic treatment, unacceptable toxicity, or withdrawal. Patients with a previous history of seizure, taking medicines known to decrease the seizure threshold, or with other risk factors for seizure were not eligible [see Warnings and Precautions (5.1)].

The following patient demographics and baseline disease characteristics were balanced between the treatment arms. The median age was 69 years (range 41-92) and the racial distribution was 92.7% White, 3.9% Black, 1.1% Asian, and 2.1% Other. Ninety-two percent of patients had an ECOG performance status score of 0-1 and 28% had a mean Brief Pain Inventory score of ≥ 4. Ninety-one percent of patients had metastases in bone and 23% had visceral involvement in the lung and/or liver. Fifty-nine percent of patients had radiographic evidence of disease progression and 41% had PSA-only progression on study entry. All patients had received prior docetaxel-based therapy and 24% had received two cytotoxic chemotherapy regimens. During the trial, 48% of patients on the XTANDI arm and 46% of patients on the placebo arm received glucocorticoids.

A statistically significant improvement in overall survival was demonstrated at the pre-specified interim analysis at the time of 520 deaths in patients on the XTANDI arm compared to patients on the placebo arm (Table 9 and Figure 1).

Table 9. Overall Survival of Patients Treated with Either XTANDI or Placebo in AFFIRM
 | XTANDI; (N = 800) | Placebo; (N = 399)
Number of Deaths (%) | 308 (38.5) | 212 (53.1)
Median Survival, months (95% CI) | 18.4 (17.3, NR) | 13.6 (11.3, 15.8)
P-value [P-value is derived from a log-rank test stratified by baseline ECOG performance status score (0-1 vs. 2) and mean baseline pain score (BPI-SF score < 4 vs. ≥ 4).] | p < 0.0001
Hazard Ratio (95% CI) [Hazard Ratio is derived from a stratified proportional hazards model. Hazard Ratio < 1 favors XTANDI.] | 0.63 (0.53, 0.75)
NR = Not reached.

Figure 1. Kaplan-Meier Curves of Overall Survival in AFFIRM

PREVAIL (NCT01212991): XTANDI versus Placebo in Chemotherapy-naïve Metastatic CRPC

In PREVAIL, 1717 chemotherapy-naïve patients were randomized 1:1 to receive either XTANDI orally at a dose of 160 mg once daily (N = 872) or placebo orally once daily (N = 845). Patients with visceral metastases, patients with a history of mild to moderate heart failure (NYHA class I or II), and patients taking medications associated with lowering the seizure threshold were allowed. Patients with a previous history of seizure or a condition that might predispose to seizure and patients with moderate or severe pain from prostate cancer were excluded. Study treatment continued until disease progression (evidence of radiographic progression, a skeletal-related event, or clinical progression) and the initiation of a cytotoxic chemotherapy or an investigational agent, unacceptable toxicity, or withdrawal. Overall survival and radiographic progression-free survival (rPFS) were assessed. Radiographic progression was assessed with the use of sequential imaging and was defined by bone scan identification of 2 or more new bone lesions with confirmation (Prostate Cancer Clinical Trials Working Group 2 criteria) and/or Response Evaluation Criteria in Solid Tumors (RECIST v 1.1) criteria for progression of soft tissue lesions. The primary analysis of rPFS utilized centrally reviewed radiographic assessment of progression.

Patient demographics and baseline disease characteristics were balanced between the treatment arms at entry. The median age was 71 years (range 42-93) and the racial distribution was 77% White, 10% Asian, 2% Black and 11% Other. The ECOG performance status score was 0 for 68% of patients, and 1 for 32% of patients. Baseline pain assessment was 0-1 (asymptomatic) in 67% of patients, and 2-3 (mildly symptomatic) in 32% of patients as defined by the Brief Pain Inventory Short Form (worst pain over past 24 hours at study entry). Fifty-four percent of patients had radiographic evidence of disease progression and 43% had PSA-only progression. Twelve percent of patients had visceral (lung and/or liver) disease involvement. During the study, 27% of patients on the XTANDI arm and 30% of patients on the placebo arm received glucocorticoids for varying reasons.

A statistically significant improvement in overall survival was demonstrated at the pre-specified interim analysis, conducted after 540 deaths, in patients treated with XTANDI compared to those treated with placebo (Table 10). Forty percent of XTANDI-treated and 70% of placebo-treated patients received subsequent therapies for metastatic CRPC that may prolong overall survival. An updated survival analysis was conducted when 784 deaths were observed. The median follow-up time was 31 months. Results from this analysis were consistent with those from the pre-specified interim analysis (Table 10, Figure 2). At the updated analysis, 52% of XTANDI-treated and 81% of placebo-treated patients had received subsequent therapies that may prolong overall survival in metastatic CRPC. XTANDI was used as a subsequent therapy in 2% of XTANDI-treated patients and 29% of placebo-treated patients.

Table 10. Overall Survival of Patients Treated with Either XTANDI or Placebo in PREVAIL
 | XTANDI; (N = 872) | Placebo; (N = 845)
Pre-specified Interim Analysis [The data cut-off date is 16 Sep 2013.]
Number of Deaths (%) | 241 (28) | 299 (35)
Median Survival, months (95% CI) | 32.4 (30.1, NR) | 30.2 (28.0, NR)
P-value [P-value is derived from an unstratified log-rank test.] | p < 0.0001
Hazard Ratio (95% CI) [Hazard Ratio is derived from an unstratified proportional hazards model. Hazard Ratio < 1 favors XTANDI.] | 0.71 (0.60, 0.84)
Updated Survival Analysis [The data cut-off date is 1 Jun 2014. The planned number of deaths for the final overall survival analysis was ≥ 765.]
Number of Deaths (%) | 368 (42) | 416 (49)
Median Survival, months (95% CI) | 35.3 (32.2, NR) | 31.3 (28.8, 34.2)
Hazard Ratio (95% CI) | 0.77 (0.67, 0.88)
NR = Not reached.

Figure 2. Kaplan-Meier Curves of Overall Survival in PREVAIL

A statistically significant improvement in rPFS was demonstrated in patients treated with XTANDI compared to patients treated with placebo (Table 11, Figure 3).

Table 11. Radiographic Progression-free Survival of Patients Treated with Either XTANDI or Placebo in PREVAIL
 | XTANDI; (N = 832) | Placebo; (N = 801)
Number of Progression or Deaths (%) | 118 (14) | 320 (40)
Median rPFS (months) (95% CI) | NR (13.8, NR) | 3.7 (3.6, 4.6)
P-value [P-value is derived from an unstratified log-rank test.] | p < 0.0001
Hazard Ratio (95% CI) [Hazard Ratio is derived from an unstratified proportional hazards model. Hazard Ratio < 1 favors XTANDI.] | 0.17 (0.14, 0.21)
NR = Not reached.
Note: As of the cut-off date for the rPFS analysis, 1633 patients had been randomized.

Figure 3. Kaplan-Meier Curves of Radiographic Progression-free Survival in PREVAIL

Time to initiation of cytotoxic chemotherapy was prolonged after XTANDI treatment, with a median of 28.0 months for patients on the XTANDI arm versus a median of 10.8 months for patients on the placebo arm [HR = 0.35 (95% CI: 0.30, 0.40), p < 0.0001].

The median time to first skeletal‑related event was 31.1 months for patients on the XTANDI arm versus 31.3 months for patients on the placebo arm [HR = 0.72 (95% CI: 0.61, 0.84), p < 0.0001]. A skeletal‑related event was defined as radiation therapy or surgery to bone for prostate cancer, pathologic bone fracture, spinal cord compression, or change of antineoplastic therapy to treat bone pain.

TERRAIN (NCT01288911): XTANDI versus Bicalutamide in Chemotherapy-naïve Metastatic CRPC

TERRAIN was conducted in 375 chemotherapy-naïve patients who were randomized 1:1 to receive either XTANDI orally at a dose of 160 mg once daily (N = 184) or bicalutamide orally at a dose of 50 mg once daily (N = 191). Patients with a previous history of seizure or a condition that might predispose to seizure and patients with moderate to severe pain from prostate cancer were excluded. Patients could have received prior bicalutamide, but those whose disease had progressed on prior antiandrogen therapy (e.g., bicalutamide) were excluded. Study treatment continued until disease progression (evidence of radiographic progression, a skeletal-related event), the initiation of subsequent antineoplastic agent, unacceptable toxicity, or withdrawal. Radiographic disease progression was assessed by Independent Central Review (ICR) using the Prostate Cancer Clinical Trials Working Group 2 criteria and/or Response Evaluation Criteria in Solid Tumors (RECIST v 1.1) criteria for progression of soft tissue lesions. Radiographic progression-free survival (rPFS) was defined as the time from randomization to the first objective evidence of radiographic progression as assessed by ICR or death, whichever occurred first.

Patient demographics and baseline disease characteristics were balanced between the treatment arms at entry. The median age was 71 years (range 48-96) and the racial distribution was 93% White, 5% Black, 1% Asian and 1% Other. The ECOG performance status score was 0 for 74% of patients and 1 for 26% of patients. Baseline pain assessment was 0‑1 (asymptomatic) in 58% of patients, and 2‑3 (mildly symptomatic) in 36% of patients as defined by the Brief Pain Inventory Short Form Question 3 (worst pain over past 24 hours at study entry). Ninety-eight percent of patients had objective evidence of disease progression at study entry. Forty-six percent of patients had received prior treatment with bicalutamide while no patients received prior treatment with XTANDI.

An improvement in rPFS was demonstrated in patients treated with XTANDI compared to patients treated with bicalutamide (Table 12, Figure 4).

Table 12. Radiographic Progression-free Survival of Patients in TERRAIN
 | XTANDI (N = 184) | Bicalutamide (N = 191)
Number of Progression or Deaths (%) | 72 (39) | 74 (39)
Median rPFS (months) (95% CI) | 19.5 (11.8, NR) | 13.4 (8.2, 16.4)
Hazard Ratio (95% CI) [Hazard Ratio is derived from an unstratified proportional hazards model. Hazard Ratio < 1 favors XTANDI.] | 0.60 (0.43, 0.83)
NR = Not reached.

Figure 4. Kaplan-Meier Curves of Radiographic Progression-free Survival in TERRAIN

PROSPER (NCT02003924): XTANDI versus Placebo in Non-metastatic CRPC

PROSPER enrolled 1401 patients with non-metastatic CRPC who were randomized 2:1 to receive either XTANDI orally at a dose of 160 mg once daily (N = 933) or placebo orally once daily (N = 468). All patients in the PROSPER trial received a gonadotropin-releasing hormone (GnRH) analog or had a prior bilateral orchiectomy. Patients were stratified by Prostate Specific Antigen (PSA) Doubling Time (PSADT) and the use of bone-targeting agents. Patients were required to have a PSA doubling time ≤ 10 months, PSA ≥ 2 ng/mL, and confirmation of non-metastatic disease by blinded independent central review (BICR). PSA results were blinded and were not used for treatment discontinuation. Patients randomized to either arm discontinued treatment for radiographic disease progression confirmed by BICR, initiation of new treatment, unacceptable toxicity, or withdrawal.

The following patient demographics and baseline characteristics were balanced between the two treatment arms. The median age at randomization was 74 years (range 50-95) and 23% were 80 years of age or older. The racial distribution was 71% White, 16% Asian, and 2% Black. A majority of patients had a Gleason score of 7 or higher (77%). The median PSADT was 3.7 months. Fifty-four percent (54%) of patients received prior treatment for prostate cancer with either surgery or radiation. Sixty-three percent (63%) of patients received prior treatment with an anti-androgen; 56% of patients received bicalutamide and 11% of patients received flutamide. All patients had an Eastern Cooperative Oncology Group Performance Status (ECOG PS) score of 0 or 1 at study entry.

The major efficacy outcome of the study was metastasis-free survival (MFS), defined as the time from randomization to whichever of the following occurred first 1) loco-regional and/or distant radiographic progression per BICR or 2) death up to 112 days after treatment discontinuation without evidence of radiographic progression. A statistically significant improvement in MFS and OS was demonstrated in patients randomized to receive XTANDI compared with patients randomized to receive placebo. Consistent MFS results were observed when considering only distant radiographic progression events or deaths regardless of the cut-off date. Consistent MFS results were also observed in pre-specified and stratified patient sub-groups of PSADT (< 6 months or ≥ 6 months) and use of a prior bone-targeting agent (yes or no). The efficacy results from PROSPER are summarized in Table 13, Figure 5 and Figure 6.

Table 13. Summary of Efficacy Results in PROSPER (Intent-to-treat Population)
 | XTANDI (N = 933) | Placebo (N = 468)
Metastasis-free survival
Number of Events (%) | 219 (23.5) | 228 (48.7)
Median, months (95% CI) [Based on Kaplan-Meier estimates.] | 36.6 (33.1, NR) | 14.7 (14.2, 15.0)
Hazard Ratio (95% CI) [Hazard ratio from a Cox regression model (with treatment as the only covariate) and p-value from a log-rank test are stratified by PSA doubling time and prior or concurrent use of a bone targeting agent.] | 0.29 (0.24, 0.35)
P-value | p < 0.0001
Overall survival [The pre-specified final analysis of OS occurred 27 months after the MFS analysis.]
Number of Events (%) | 288 (30.9) | 178 (38.0)
Median, months (95% CI) | 67.0 (64.0, NR) | 56.3 (54.4, 63.0)
Hazard Ratio (95% CI) | 0.73 (0.61, 0.88)
P-value | p = 0.0011
NR = Not reached.

Figure 5. Kaplan-Meier Curves of Metastasis-free Survival in PROSPER
Figure 6. Kaplan-Meier Curves of Overall Survival in PROSPER

The primary efficacy outcome was also supported by a statistically significant delay in time to first use of new antineoplastic therapy (TTA) for patients in the XTANDI arm compared to those in the placebo arm. The median TTA was 39.6 months for patients on XTANDI and was 17.7 months for patients on placebo (HR = 0.21; 95% CI: [0.17, 0.26], p < 0.0001).

ARCHES (NCT02677896): XTANDI versus Placebo in Metastatic CSPC

ARCHES enrolled 1150 patients with mCSPC who were randomized 1:1 to receive XTANDI orally at a dose of 160 mg once daily (N = 574) or placebo orally once daily (N = 576). All patients in the trial received a GnRH analog or had a prior bilateral orchiectomy. Patients were stratified by volume of disease (low vs high) and prior docetaxel therapy for prostate cancer (no prior docetaxel, 1-5 cycles, or 6 prior cycles). High volume of disease is defined as metastases involving the viscera or, in the absence of visceral lesions, there must be 4 or more bone lesions, at least 1 of which must be in a bony structure beyond the vertebral column and pelvic bone. Treatment with concurrent docetaxel was not allowed. Patients continued treatment until radiographic disease progression, initiation of new treatment, unacceptable toxicity, or withdrawal.

The following patient demographics and baseline characteristics were balanced between the two treatment arms. The median age at randomization was 70 years (range: 42-92) and 30% were 75 years of age or older. The racial distribution was 81% White, 14% Asian, and 1% Black. Sixty-six percent (66%) of patients had a Gleason score of ≥ 8. Thirty-seven percent (37%) of patients had a low volume of disease and 63% of patients had a high volume of disease. Eighty-two percent (82%) of patients had no prior docetaxel treatment; 2% of patients had 1 to 5 cycles of docetaxel and 16% of patients had 6 prior cycles of docetaxel treatment. Twelve percent (12%) of patients received concomitant bone-targeted agents (bisphosphonates or RANKL inhibitors) which included both prostate and non-prostate cancer indications. The Eastern Cooperative Oncology Group Performance Status (ECOG PS) score was 0 for 78% of patients and 1 for 22% of patients at study entry.

The major efficacy outcome measure was radiographic progression-free survival (rPFS) based on blinded independent central review (BICR). Radiographic progression-free survival was defined as the time from randomization to radiographic disease progression at any time or death within 24 weeks after study drug discontinuation. Radiographic disease progression was defined by identification of 2 or more new bone lesions on a bone scan with confirmation (Prostate Cancer Working Group 2 criteria) and/or progression in soft tissue disease. Time to new antineoplastic therapy and OS were additional efficacy endpoints.

XTANDI demonstrated a statistically significant improvement in rPFS and OS compared to placebo. Consistent rPFS results were observed in patients with high or low volume of disease and patients with and without prior docetaxel therapy. Efficacy results for rPFS and OS from ARCHES are summarized in Table 14, Figure 7 and Figure 8.

Table 14. Efficacy Results in ARCHES (Intent-to-Treat Analysis)
 | XTANDI (N = 574) | Placebo (N = 576)
Radiographic Progression-free Survival [Based on BICR.]
Number of events (%) | 89 (15.5) | 198 (34.4)
Radiographic disease progression | 77 (13.4) | 185 (32.1)
Death within 24 weeks after treatment discontinuation | 12 (2.1) | 13 (2.3)
Median, months (95% CI) [Based on Kaplan-Meier estimates.] | NR | 19.4 (16.6, NR)
Hazard ratio (95% CI) [Hazard Ratio is based on a Cox regression model stratified by volume of disease (low vs high) and prior docetaxel use (yes vs no).] | 0.39 (0.30, 0.50)
P-value [P-value is based on a stratified log-rank test by volume of disease (low vs high) and prior docetaxel use (yes or no).] | p < 0.0001
Overall Survival
Number of events (%) | 154 (26.8) | 202 (35.1)
Median, months (95% CI) | NR (NR, NR) | NR (49.7, NR)
Hazard ratio (95% CI) | 0.66 (0.53, 0.81)
P-value | p < 0.0001
NR = Not reached.

Figure 7. Kaplan-Meier Curves of rPFS in ARCHES (Intent-to-Treat Analysis)
Figure 8. Kaplan-Meier Curves of Overall Survival in ARCHES

A statistically significant improvement was also reported on the XTANDI arm compared to placebo in time to initiation of a new antineoplastic therapy (HR = 0.28 [95% CI: 0.20, 0.40]; p < 0.0001).

EMBARK (NCT02319837): XTANDI versus Placebo in Non-metastatic CSPC with High-Risk BCR

EMBARK enrolled 1068 patients with nmCSPC with high-risk BCR who were randomized 1:1:1 to receive XTANDI orally at a dose of 160 mg once daily concurrently with leuprolide (N = 355), XTANDI orally at a dose of 160 mg once daily as open‑label as a single agent (N = 355), or placebo orally once daily concurrently with leuprolide (N = 358). All patients had prior definitive therapy with radical prostatectomy or radiotherapy (including brachytherapy) with curative intent, or both. Patients were not candidates for salvage radiotherapy at the time of enrollment. Patients were required to have confirmation of non-metastatic disease by BICR, high‑risk BCR (defined by a PSA doubling time ≤ 9 months), and PSA values ≥1 ng/mL if they had prior radical prostatectomy (with or without radiotherapy) as the primary treatment for prostate cancer or PSA values at least 2 ng/mL above the nadir if they had prior radiotherapy only.

Patients were stratified by screening PSA (≤10 ng/mL vs. >10 ng/mL), PSA doubling time (≤3 months versus >3 months to ≤ 9 months), and prior hormonal therapy. For patients whose PSA values were undetectable (<0.2 ng/mL) at week 36, treatment was suspended at week 37 and then reinitiated when PSA values increased to ≥2.0 ng/mL for patients with prior prostatectomy or ≥5.0 ng/mL for patients without prior prostatectomy. For patients whose PSA values were detectable (≥0.2 ng/mL) at week 36, treatment continued without suspension until permanent treatment discontinuation criteria were met. For all patients, treatment was permanently discontinued upon radiographic disease progression confirmed by BICR, initiation of new treatment, unacceptable toxicity, or withdrawal.

The median age at randomization was 69 years (range: 49-93) and 23% were 75 years of age or older. The racial distribution was 83% White, 7% Asian, 4% Black, 2.3% Others, and 2.7% not reported; 5.5% of patients were Hispanic or Latino. The median PSADT was 4.9 months. Seventy-four percent (74%) of patients had prior definitive therapy with radical prostatectomy, 34% of patients had prior primary radiotherapy (including brachytherapy), and 49% of patients had prior therapy with both surgery and radiotherapy (including adjuvant and salvage radiotherapy). Thirty-two percent (32%) of patients had a Gleason score of ≥ 8. The ECOG PS score was 0 for 92% of patients and 1 for 8% of patients at study entry.

The major efficacy outcome measure was metastasis-free survival (MFS) in patients randomized to receive XTANDI plus leuprolide compared to patients randomized to receive placebo plus leuprolide. MFS was defined as the time from randomization to whichever of the following occurred first 1) radiographic progression per BICR or 2) death. MFS in patients randomized to receive XTANDI as a single agent compared to patients randomized to receive placebo plus leuprolide and overall survival (OS) were additional efficacy outcome measures.

A statistically significant improvement in MFS was demonstrated in patients randomized to receive XTANDI plus leuprolide compared with patients randomized to receive placebo plus leuprolide. A statistically significant improvement in MFS was also demonstrated in patients randomized to receive XTANDI as a single agent compared with patients randomized to receive placebo plus leuprolide. The results are summarized in Table 15 and Figure 9.

Table 15. Metastasis-free Survival Based on BICR in EMBARK (Intent-to-treat Population)
 | XTANDI; +; Leuprolide (N = 355) | Placebo; +; Leuprolide (N = 358) | XTANDI; (N = 355)
Metastasis-free survival
Number of Events (%) [Based on the earliest contributing event (radiographic progression or death).] | 45 (12.7) | 92 (25.7) | 63 (17.7)
Median, months (95% CI) [Based on Kaplan-Meier estimates.] | NR (NR, NR) | NR (85.1, NR) | NR (NR, NR)
Hazard Ratio relative to Placebo plus Leuprolide (95% CI) [Hazard Ratio is based on a Cox regression model stratified by screening PSA, PSA doubling time, and prior hormonal therapy.] | 0.42 (0.30, 0.61) | -- | 0.63 (0.46, 0.87)
P-value for comparison to Placebo + Leuprolide [Two-sided P-value is based on a stratified log-rank test by screening PSA, PSA doubling time, and prior hormonal therapy.] | p < 0.0001 | -- | p = 0.0049
NR = Not reached.

Figure 9. Kaplan-Meier Curves of Metastasis-free Survival in the XTANDI plus Leuprolide vs. Placebo plus Leuprolide vs. XTANDI Treatment Arms in EMBARK

OS data were not mature at the time of MFS analysis (12.2% deaths across the overall population of 1068 patients).

16 HOW SUPPLIED/STORAGE AND HANDLING

XTANDI (enzalutamide) 40 mg capsules are supplied as white to off-white oblong soft gelatin capsules imprinted in black ink with ENZ and are available in the following package size:

- Bottles of 120 capsules with child resistant closures (NDC 0469-0125-99)

XTANDI (enzalutamide) 40 mg tablets are supplied as yellow, round, film-coated tablets debossed with E 40, and are available in the following package size:

- Bottles of 120 tablets with child resistant closures (NDC 0469-0625-99)

XTANDI (enzalutamide) 80 mg tablets are supplied as yellow, oval, film-coated tablets debossed with E 80, and are available in the following package size:

- Bottles of 60 tablets with child resistant closures (NDC 0469-0725-60)

Store XTANDI capsules and tablets at 20°C to 25°C (68°F to 77°F) in a dry place and keep the container tightly closed. Excursions permitted from 15°C to 30°C (59°F to 86°F).

17 PATIENT COUNSELING INFORMATION

Advise the patient to read the FDA-approved patient labeling (Patient Information).

Seizure

- Inform patients that XTANDI has been associated with an increased risk of seizure. Discuss conditions that may predispose to seizures and medications that may lower the seizure threshold. Advise patients of the risk of engaging in any activity where sudden loss of consciousness could cause serious harm to themselves or others. Inform patients to contact their healthcare provider right away if they have loss of consciousness or seizure [see Warnings and Precautions (5.1)].

Posterior Reversible Encephalopathy Syndrome (PRES)

- Inform patients to contact their healthcare provider right away if they experience rapidly worsening symptoms possibly indicative of PRES such as seizure, headache, decreased alertness, confusion, reduced eyesight, or blurred vision [see Warnings and Precautions (5.2)].

Hypersensitivity

- Inform patients that XTANDI may be associated with hypersensitivity reactions that include swelling of the face, lip, tongue, or throat [see Warnings and Precautions (5.3)]. Advise patients who experience these types of symptoms of hypersensitivity to discontinue XTANDI and promptly contact their healthcare provider.

Ischemic Heart Disease

- Inform patients that XTANDI has been associated with an increased risk of ischemic heart disease. Advise patients to seek immediate medical attention if any symptoms suggestive of a cardiovascular event occur [see Warnings and Precautions (5.4)].

Falls and Fractures

- Inform patients that XTANDI is associated with an increased incidence of dizziness/vertigo, falls, and fractures. Advise patients to report these adverse reactions to their healthcare provider [see Warnings and Precautions (5.5)].

Dysphagia or Choking

- Inform patients that the size of XTANDI capsules and tablets has been associated with severe dysphagia or choking.
- Advise patients to take each capsule or tablet as instructed in Dosage and Administration.
- Advise patients to inform their healthcare provider if experiencing difficulty swallowing XTANDI [see Warnings and Precautions (5.7)].

Hypertension

- Inform patients that XTANDI is associated with an increased incidence of hypertension [see Adverse Reactions (6.1)].

Dosage and Administration

- Inform patients who have not undergone bilateral orchiectomy and are receiving GnRH therapy that they need to maintain this treatment during the course of treatment with XTANDI.
- Instruct patients to take their dose at the same time each day (once daily). XTANDI can be taken with or without food. Advise patients to take each capsule or tablet whole with a sufficient amount of water to ensure that all medication is successfully swallowed. Do not chew, dissolve, or open the capsules. Do not cut, crush, or chew the tablets [see Warnings and Precautions (5.7)].
- Inform patients that they should not interrupt, modify the dose, or stop XTANDI without first consulting their healthcare provider.
- Inform patients that if they miss a dose, then they should take it as soon as they remember. If they forget to take the dose for the whole day, then they should take their normal dose the next day. They should not take more than their prescribed dose per day [see Dosage and Administration (2.1)].

Embryo-Fetal Toxicity

- Inform patients that XTANDI can be harmful to a developing fetus and can cause loss of pregnancy.
- Advise male patients with female partners of reproductive potential to use effective contraception during treatment and for 3 months after the last dose of XTANDI. Advise male patients to use a condom if having sex with a pregnant woman [see Warnings and Precautions (5.6)].

Infertility

- Inform male patients that XTANDI may impair fertility [see Use in Specific Populations (8.3)].

Drug Interactions

- Advise patients to inform their healthcare providers of all concomitant medications, including prescription medicines, over-the-counter drugs, and herbal products [see Drug Interactions (7.1, 7.2, 7.3)].

Manufactured for and Distributed by: Astellas Pharma US, Inc., Northbrook, IL 60062

Marketed by:
Astellas Pharma US, Inc., Northbrook, IL 60062 Pfizer Inc., New York, NY 10001
CR-02515-XTA-USA

Rx Only
© 2025 Astellas Pharma Inc. or its affiliates

PATIENT INFORMATION

XTANDI® (ex TAN dee)

(enzalutamide)

capsules

XTANDI® (ex TAN dee)

(enzalutamide)

tablets

What is XTANDI®?

XTANDI is a prescription medicine used to treat men with prostate cancer that:

- no longer responds to a hormone therapy or surgical treatment to lower testosterone
OR
- has spread to other parts of the body and responds to a hormone therapy or surgical treatment to lower testosterone
  OR
- has not spread to other parts of the body and responds to a hormone therapy or surgical treatment to lower testosterone, and who are at high risk of cancer spreading to other parts of the body

It is not known if XTANDI is safe and effective in females.

It is not known if XTANDI is safe and effective in children.

Before taking XTANDI, tell your healthcare provider about all your medical conditions, including if you:

- have a history of seizures, brain injury, stroke, or brain tumors.
- have a history of heart disease.
- have high blood pressure.
- have abnormal amounts of fat or cholesterol in your blood (dyslipidemia).
- are pregnant or plan to become pregnant. XTANDI can cause harm to your unborn baby and loss of pregnancy (miscarriage).
- have a partner who is pregnant or may become pregnant.
  - Males who have female partners who are able to become pregnant should use effective birth control (contraception) during treatment with XTANDI and for 3 months after the last dose of XTANDI.
  - Males must use a condom during sex with a pregnant female.
- are breastfeeding or plan to breastfeed. It is not known if XTANDI passes into your breast milk.

Tell your healthcare provider about all the medicines you take, including prescription and over-the-counter medicines, vitamins, and herbal supplements. XTANDI may affect the way other medicines work, and other medicines may affect how XTANDI works.

You should not start or stop any medicine before you talk with the healthcare provider that prescribed XTANDI.

Know the medicines you take. Keep a list of them with you to show your healthcare provider and pharmacist when you get a new medicine.

How should I take XTANDI?

- Take XTANDI exactly as your healthcare provider tells you.
- Take your prescribed dose of XTANDI 1 time a day, at the same time each day.
- Your healthcare provider may change your dose if needed.
- Do not change or stop taking your prescribed dose of XTANDI without talking with your healthcare provider first.
- XTANDI can be taken with or without food.
- Swallow each XTANDI capsule or tablet whole with enough water to make sure that you can swallow all of the medicine successfully. Do not chew, dissolve, or open the capsules. Do not cut, crush, or chew the tablets. Your healthcare provider may change your treatment to a smaller tablet size or stop your treatment with XTANDI if you have swallowing problems with capsules or tablets.
- If you are receiving gonadotropin-releasing hormone (GnRH) therapy, you should continue with this treatment during your treatment with XTANDI unless you have had a surgery to lower the amount of testosterone in your body (surgical castration).
- If you miss a dose of XTANDI, take your prescribed dose as soon as you remember that day. If you miss your daily dose, take your prescribed dose at your regular time the next day. Do not take more than your prescribed dose of XTANDI each day.
- If you take too much XTANDI, call your healthcare provider or go to the nearest emergency room right away. You may have an increased risk of seizure if you take too much XTANDI.

What are the possible side effects of XTANDI?

XTANDI may cause serious side effects including:

- Seizure. If you take XTANDI you may be at risk of having a seizure. You should avoid activities where a sudden loss of consciousness could cause serious harm to yourself or others. Tell your healthcare provider right away if you have loss of consciousness or seizure.
- Posterior Reversible Encephalopathy Syndrome (PRES). If you take XTANDI you may be at risk of developing a condition involving the brain called PRES. Tell your healthcare provider right away if you have a seizure or quickly worsening symptoms such as headache, decreased alertness, confusion, reduced eyesight, blurred vision or other visual problems. Your healthcare provider will do a test to check for PRES.
- Allergic Reactions. Allergic reactions have happened in people who take XTANDI. Stop taking XTANDI and get medical help right away if you develop swelling of the face, tongue, lip or throat.
- Heart disease. Blockage of the arteries in the heart (ischemic heart disease) that can lead to death has happened in some people during treatment with XTANDI. Your healthcare provider will monitor you for signs and symptoms of heart problems during your treatment with XTANDI. Call your healthcare provider or go to the nearest emergency room right away if you get chest pain or discomfort at rest or with activity or shortness of breath during your treatment with XTANDI.
- Falls and bone fractures. XTANDI treatment may increase your risk for falls and bone fractures. Falls were not caused by loss of consciousness (fainting) or seizures. Your healthcare provider will monitor your risks for falls and bone fractures during treatment with XTANDI.
- Swallowing problems or choking. Severe swallowing problems or choking, including life-threatening problems or death can happen in people during treatment with XTANDI because of the size of the XTANDI capsules and tablets. Swallow each XTANDI capsule or tablet whole with enough water to make sure that you can swallow all of the medicine successfully. See “How should I take XTANDI?”

Your healthcare provider will stop treatment with XTANDI if you have serious side effects.

The most common side effects of XTANDI include:

- muscle and joint pain
- feeling more tired than usual
- hot flashes
- constipation
- decreased appetite
- diarrhea

- high blood pressure
- bleeding problems
- falls
- bone fractures
- headache

XTANDI may cause fertility problems in males, which may affect the ability to father children. Talk to your healthcare provider if you have concerns about fertility.

These are not all of the possible side effects of XTANDI. Call your doctor for medical advice about side effects. You may report side effects to FDA at 1-800-FDA-1088.

How should I store XTANDI?

- XTANDI capsules and tablets come in a child-resistant bottle.
- Store XTANDI capsules and tablets between 68°F to 77°F (20°C to 25°C).
- Keep XTANDI capsules and tablets dry and in a tightly closed container.

Keep XTANDI and all medicines out of the reach of children.

General information about the safe and effective use of XTANDI.

Medicines are sometimes prescribed for purposes other than those listed in a Patient Information leaflet. Do not use XTANDI for a condition for which it was not prescribed. Do not give XTANDI to other people, even if they have the same symptoms that you have. It may harm them. You can ask your healthcare provider or pharmacist for information about XTANDI that is written for health professionals.

What are the ingredients in XTANDI?

XTANDI capsules

Active ingredient: enzalutamide

Inactive ingredients: caprylocaproyl polyoxylglycerides, butylated hydroxyanisole, butylated hydroxytoluene, gelatin, sorbitol sorbitan solution, glycerin, purified water, titanium dioxide, black iron oxide.

XTANDI tablets

Active ingredient: enzalutamide

Inactive ingredients: hypromellose acetate succinate, microcrystalline cellulose, colloidal silicon dioxide, croscarmellose sodium, and magnesium stearate.

The tablet film-coat contains hypromellose, talc, polyethylene glycol, titanium dioxide, and ferric oxide.

Manufactured for and Distributed by: Astellas Pharma US, Inc., Northbrook, IL 60062
Marketed by: Astellas Pharma US, Inc., Northbrook, IL 60062 Pfizer Inc., New York, NY 10001
430539-XTA-USA
© 2025 Astellas Pharma Inc. or its affiliates
For more information go to www.Xtandi.com or call 1-800-727-7003.

This Patient Information has been approved by the U.S. Food and Drug Administration. Revised: Mar 2025

PACKAGE/LABEL PRINCIPAL DISPLAY PANEL

NDC 0469-0125-99

Rx Only

Xtandi®
(enzalutamide)
capsules

40 mg

Swallow capsules whole with a sufficient
amount of water. Do not chew,
dissolve, or open the capsules.

120 Capsules

Manufactured by
Catalent Pharma Solutions, LLC for
Astellas Pharma US, Inc.,
Northbrook, IL 60062

111607-04

415196-XTA-USA

4006396

PACKAGE/LABEL PRINCIPAL DISPLAY PANEL

NDC 0469-0625-99

Rx Only

Xtandi®
(enzalutamide)
tablets

40 mg

Swallow tablets whole with a
sufficient amount of water. Do not
cut, crush or chew the tablets.

120 Tablets

Distributed by Astellas Pharma US, Inc., Northbrook, IL 60062

75104449

415196-XTA-USA

4006397

PACKAGE/LABEL PRINCIPAL DISPLAY PANEL

NDC 0469-0725-60

Rx Only

Xtandi®
(enzalutamide)
tablets

80 mg

Swallow tablets whole with a
sufficient amount of water. Do not
cut, crush, or chew the tablets.

60 Tablets

Distributed by Astellas Pharma US, Inc., Northbrook, IL 60062

75104452

415196-XTA-USA

4006399

PACKAGE/LABEL PRINCIPAL DISPLAY PANEL

NDC 0469-1125-56

Rx Only

Xtandi®

40 mg

56 Soft Capsules

SAMPLE

SAMPLE – NOT FOR SALE

PACKAGE/LABEL PRINCIPAL DISPLAY PANEL

NDC 0469-1725-56

Rx Only

Xtandi®
(enzalutamide)
tablets

40 mg

Swallow tablets whole with a
sufficient amount of water. Do not
cut, crush, or chew the tablets.

56 Tablets

Sample – Not for Sale

Distributed by Astellas Pharma US, Inc., Northbrook, IL 60062

75104450

415196-XTA-USA

4006398